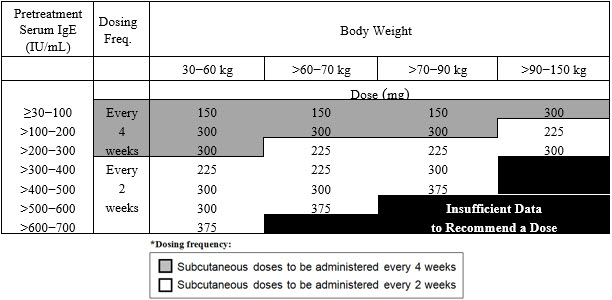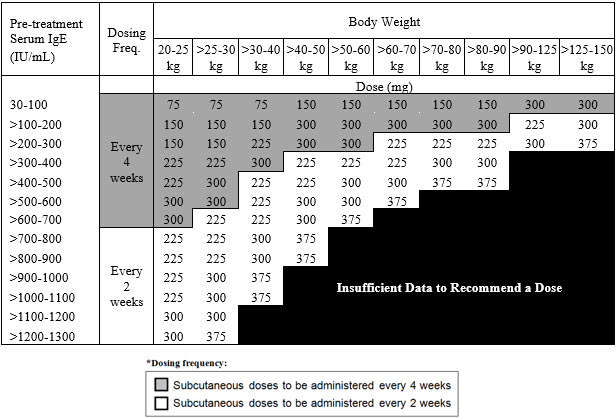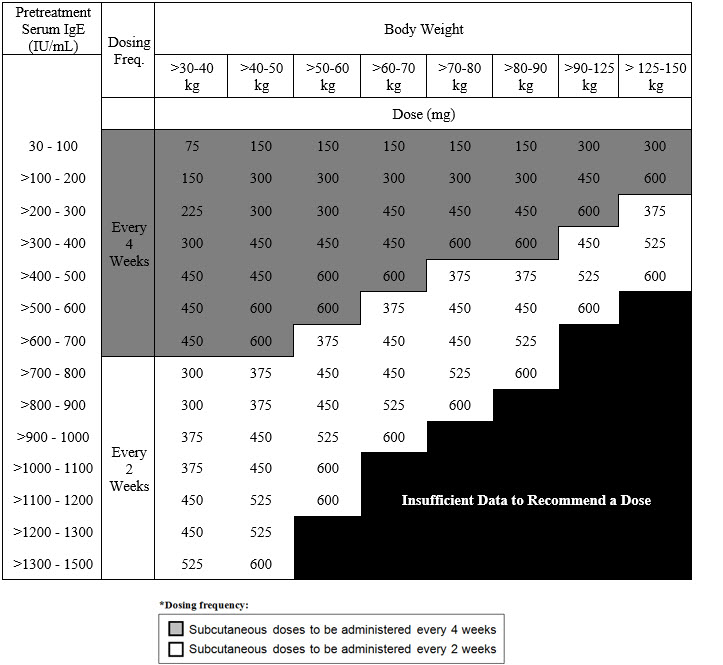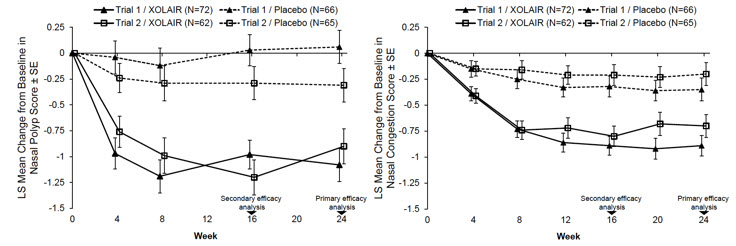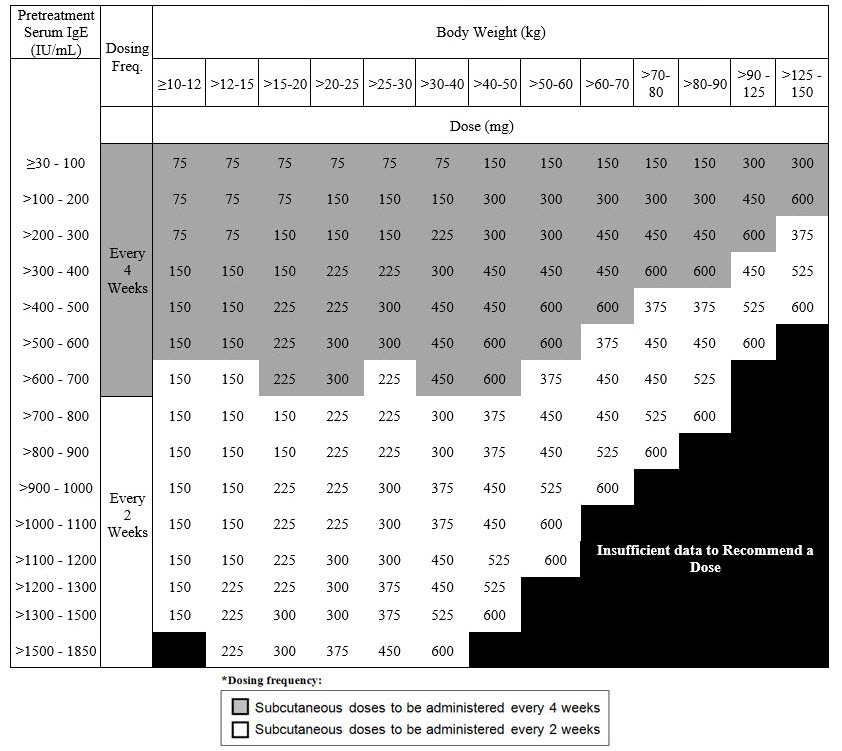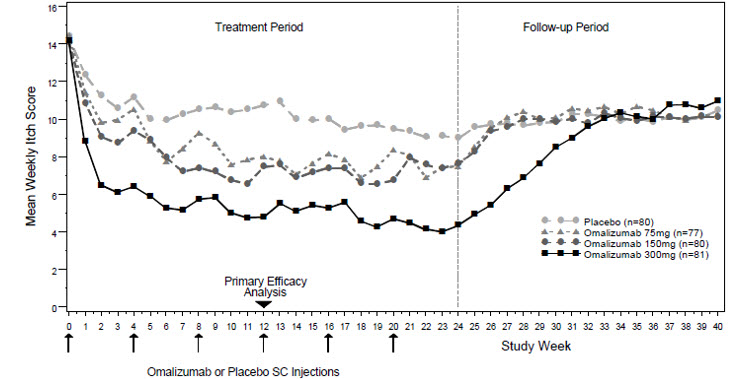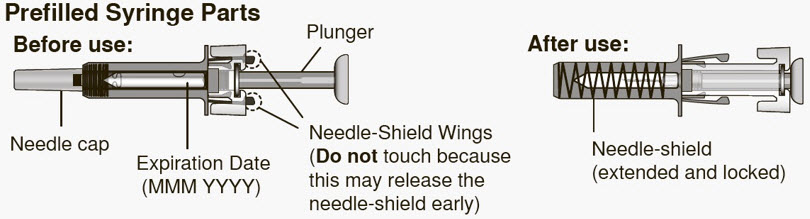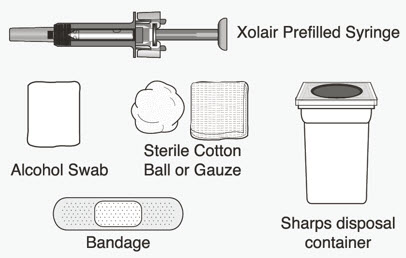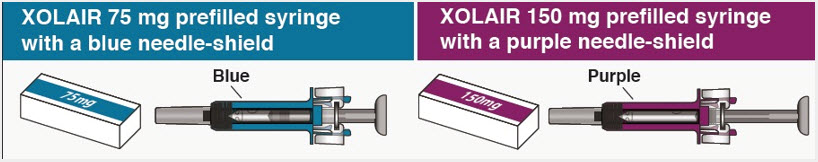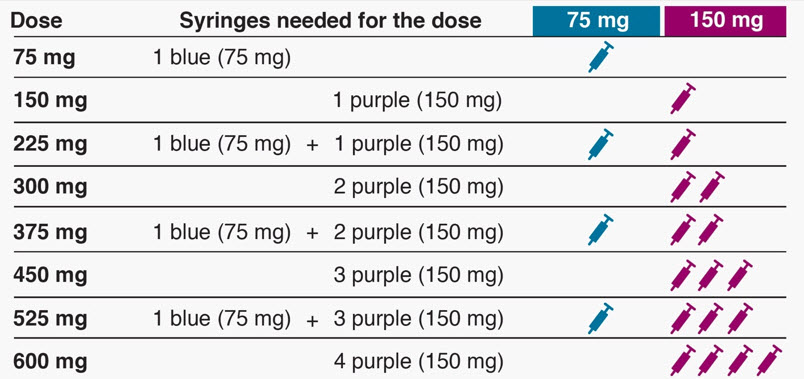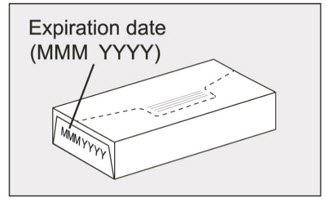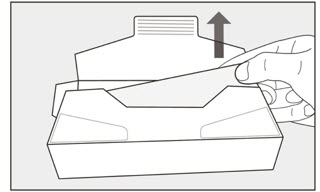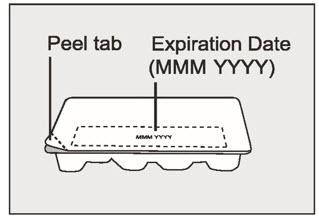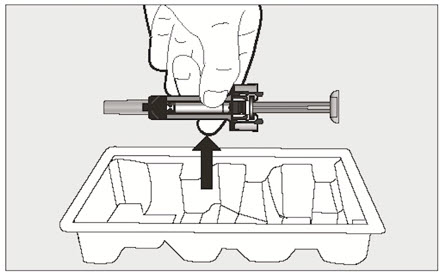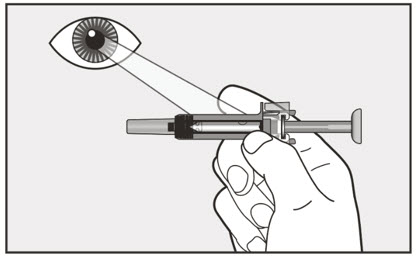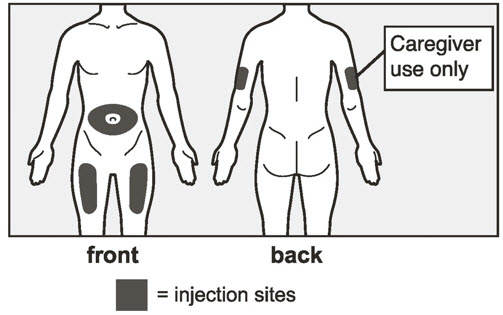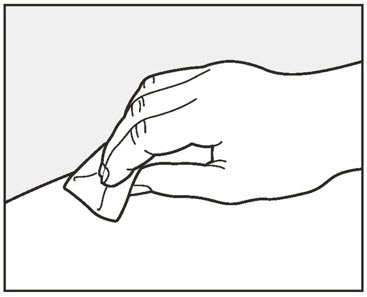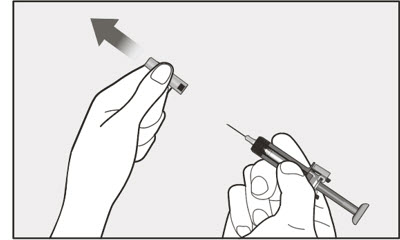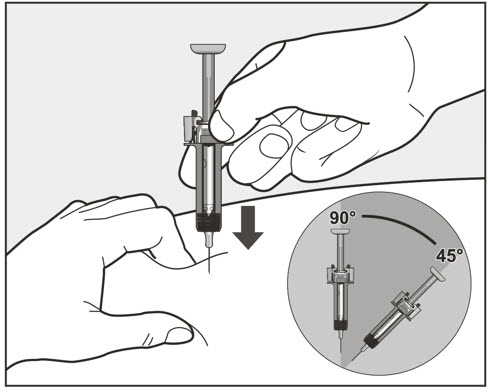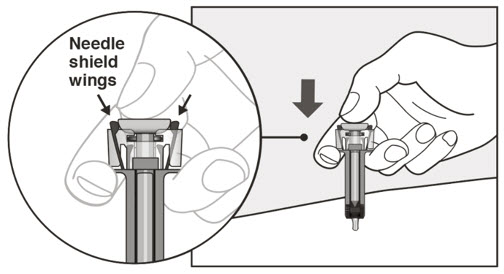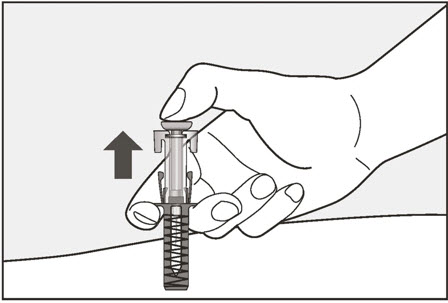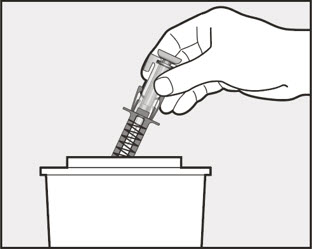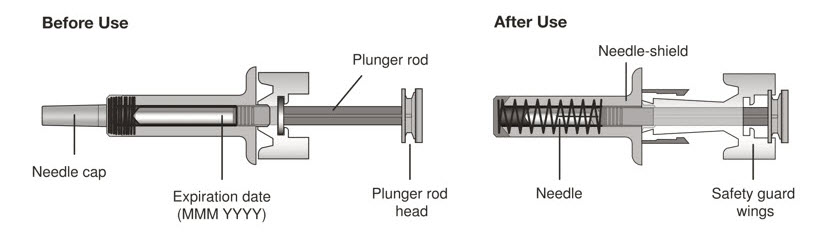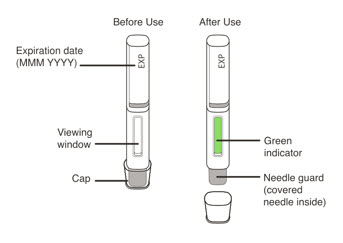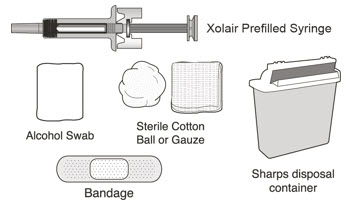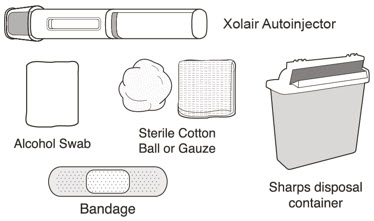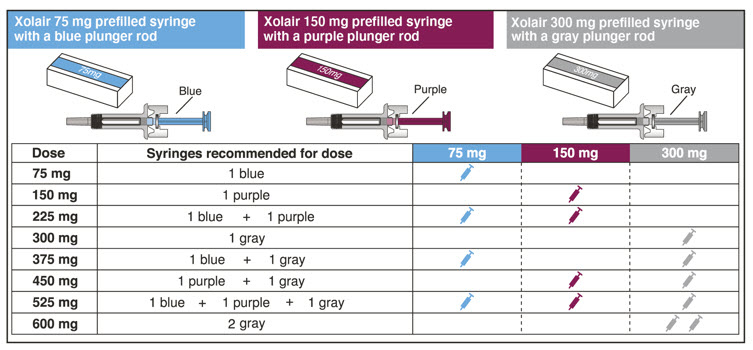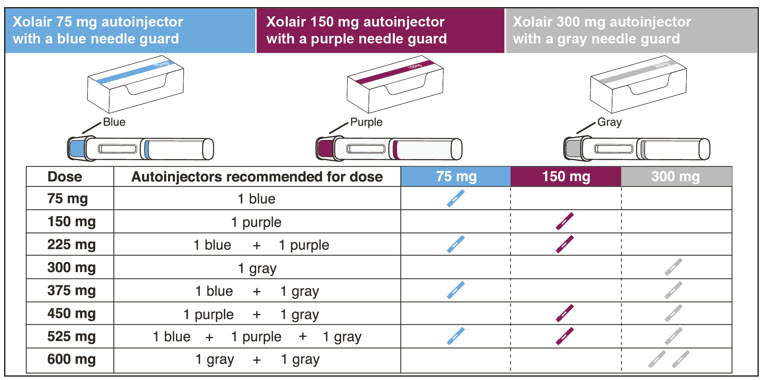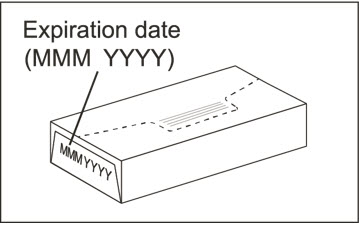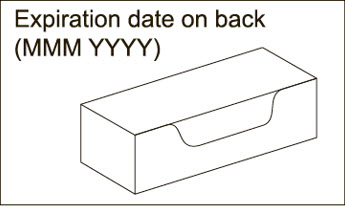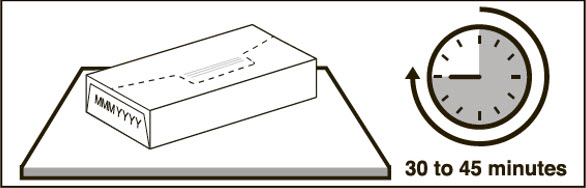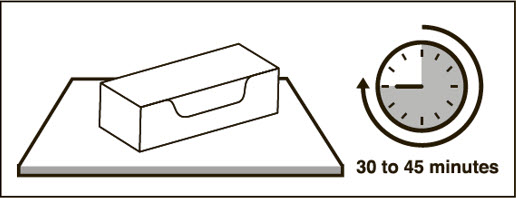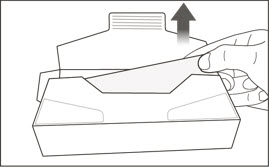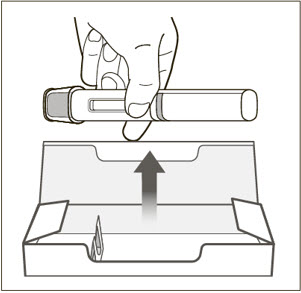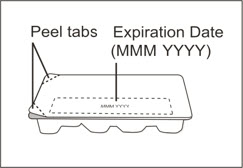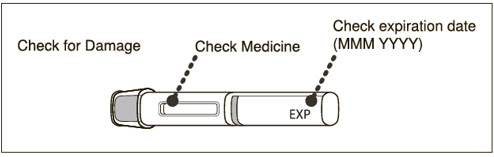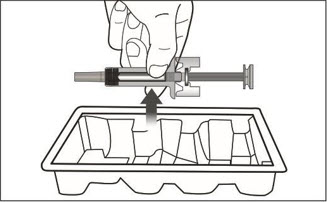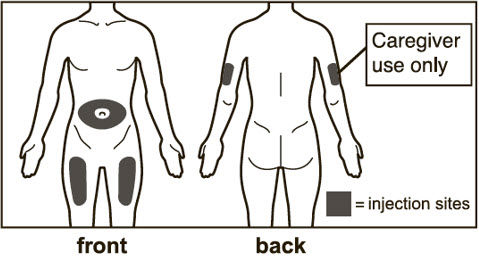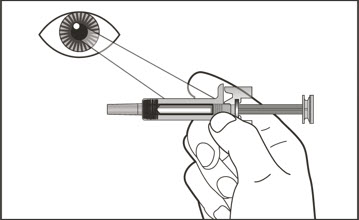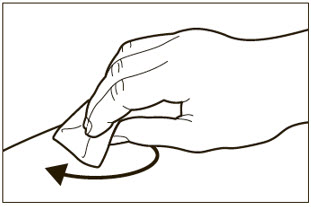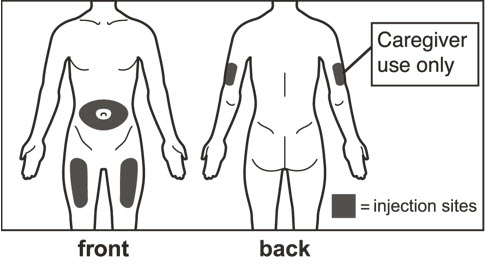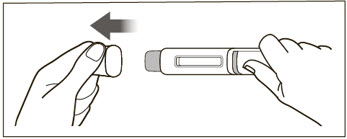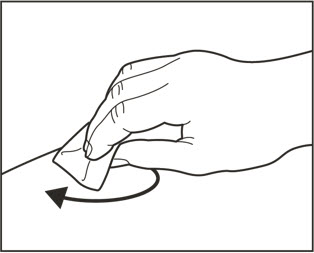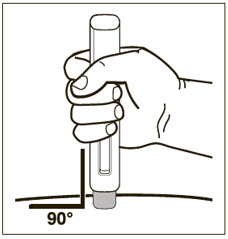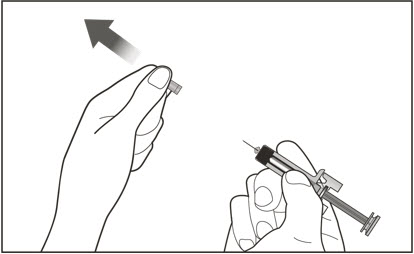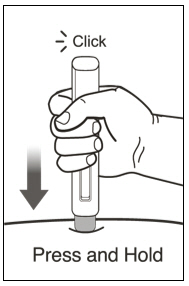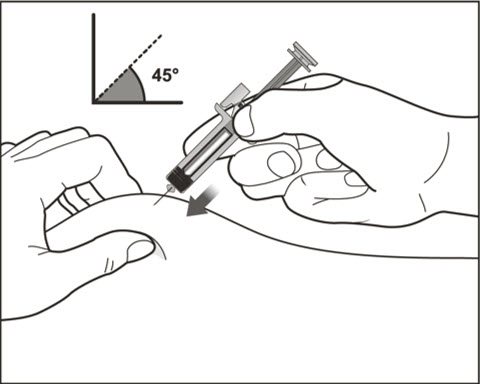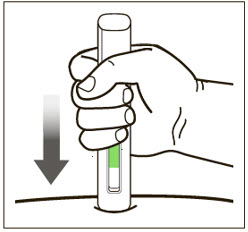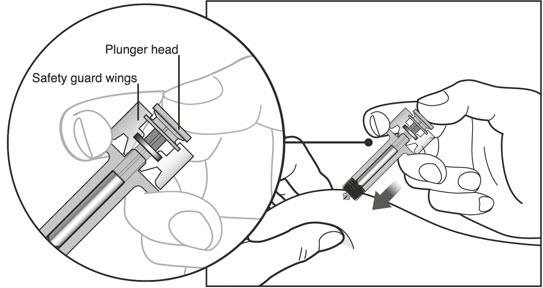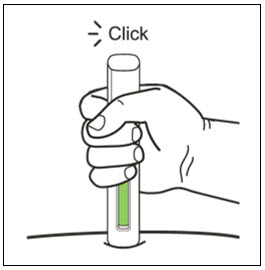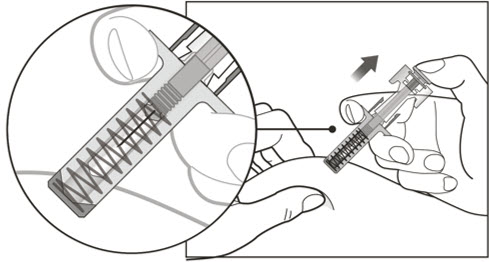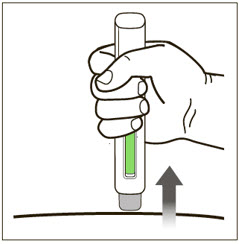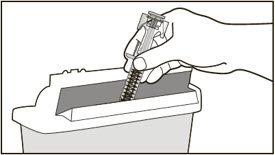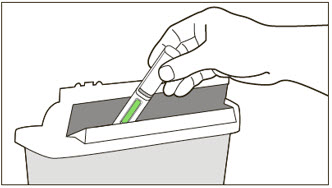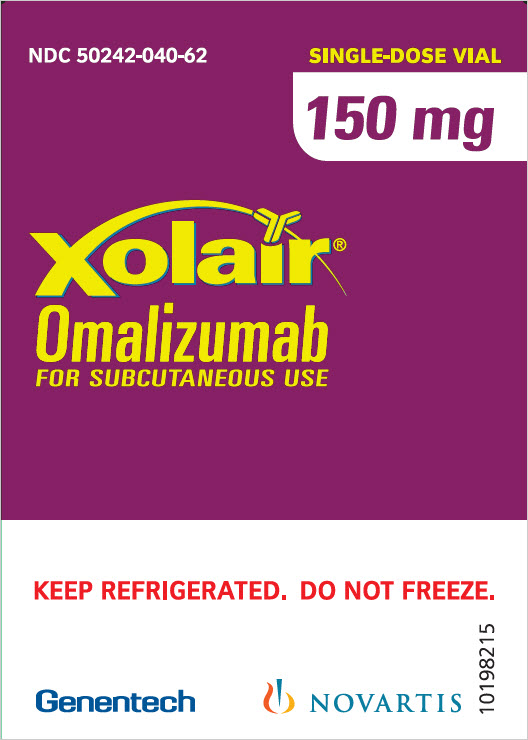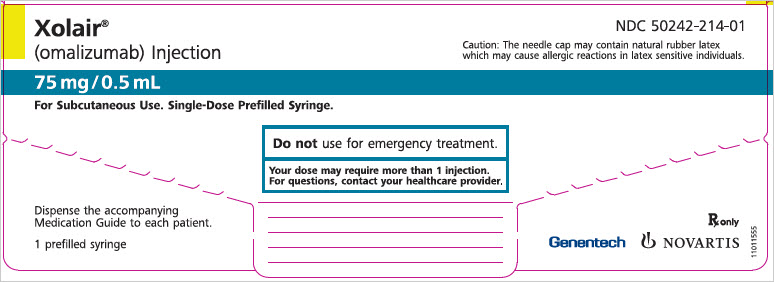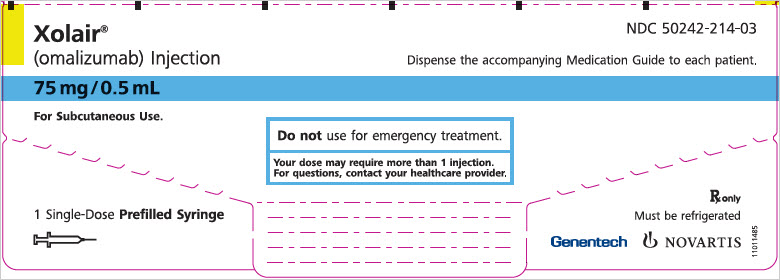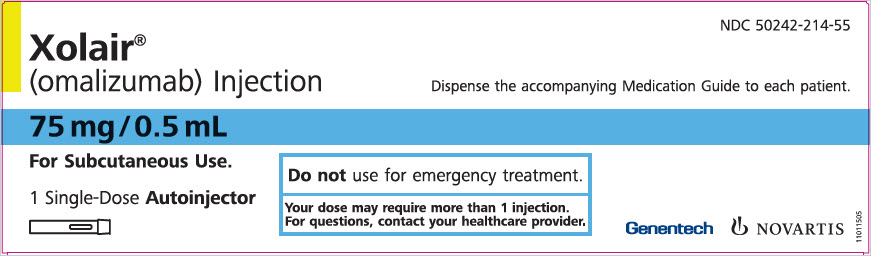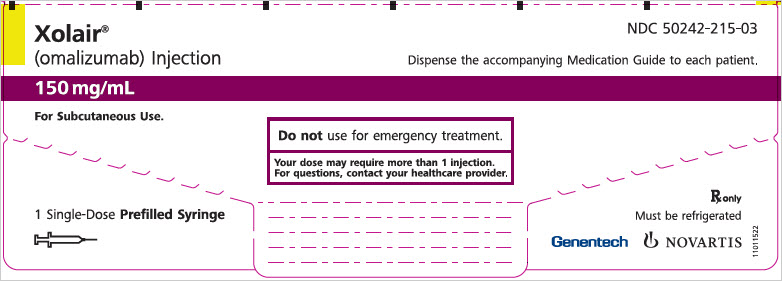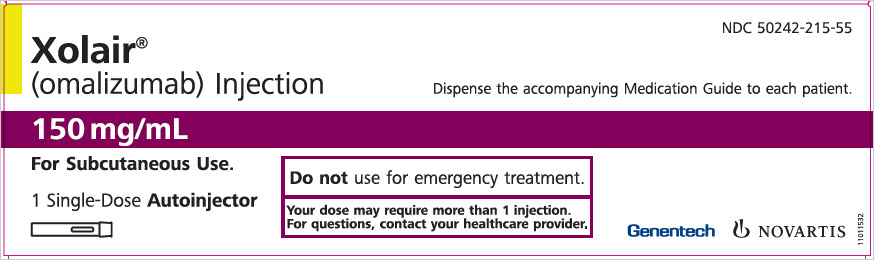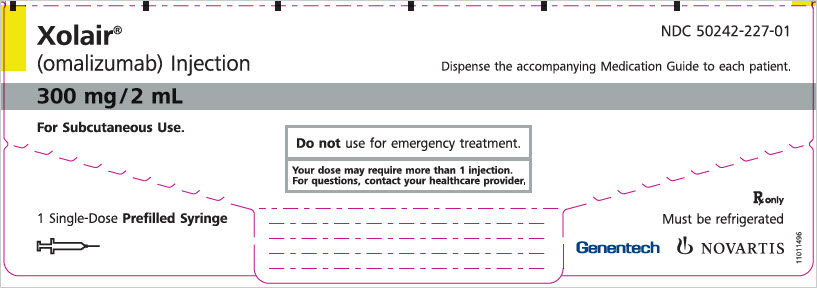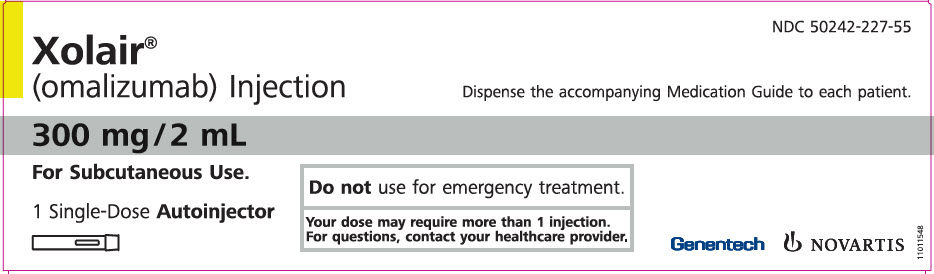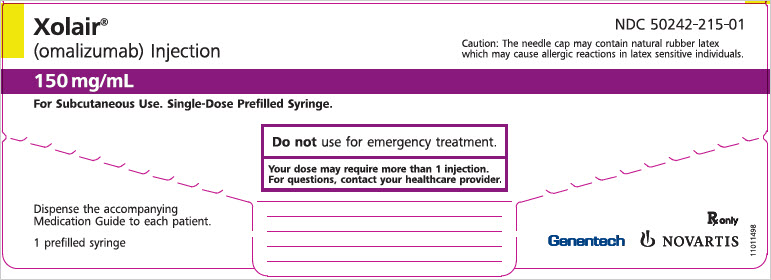 DRUG LABEL: XOLAIR
NDC: 50242-040 | Form: INJECTION, SOLUTION
Manufacturer: Genentech, Inc.
Category: prescription | Type: HUMAN PRESCRIPTION DRUG LABEL
Date: 20251202

ACTIVE INGREDIENTS: OMALIZUMAB 150 mg/1.2 mL
INACTIVE INGREDIENTS: SUCROSE 108 mg/1.2 mL; HISTIDINE HYDROCHLORIDE MONOHYDRATE 2.1 mg/1.2 mL; HISTIDINE 1.3 mg/1.2 mL; POLYSORBATE 20 0.4 mg/1.2 mL

HIGHLIGHTS OF PRESCRIBING INFORMATION

These highlights do not include all the information needed to use XOLAIR safely and effectively. See full prescribing information for XOLAIR.
XOLAIR® (omalizumab) injection, for subcutaneous use
XOLAIR® (omalizumab) for injection, for subcutaneous use
Initial U.S. Approval: 2003

WARNING: ANAPHYLAXIS

See full prescribing information for complete boxed warning.

Anaphylaxis, presenting as bronchospasm, hypotension, syncope, urticaria, and/or angioedema of the throat or tongue, has been reported to occur after administration of XOLAIR. Anaphylaxis has occurred after the first dose of XOLAIR but also has occurred beyond 1 year after beginning treatment. Initiate XOLAIR therapy in a healthcare setting, closely observe patients for an appropriate period of time after XOLAIR administration and be prepared to manage anaphylaxis which can be life-threatening. Inform patients of the signs and symptoms of anaphylaxis and have them seek immediate medical care should symptoms occur. Selection of patients for self-administration of XOLAIR should be based on criteria to mitigate risk from anaphylaxis. (2.6, 5.1, 6.1, 6.2)

RECENT MAJOR CHANGES

Indications and Usage, IgE-Mediated Food Allergy (1.3) | 2 /2024
Dosage and Administration (2.1, 2.3, 2.4, 2.5, 2.6, 2.7, 2.8) | 2 /2024
Warnings and Precautions (5.1, 5.8, 5.9) | 2 /2024

1 INDICATIONS AND USAGE

XOLAIR is an anti-IgE antibody indicated for:

- Moderate to severe persistent asthma in adults and pediatric patients 6 years of age and older with a positive skin test or in vitro reactivity to a perennial aeroallergen and symptoms that are inadequately controlled with inhaled corticosteroids (1.1)
- Chronic rhinosinusitis with nasal polyps (CRSwNP) in adult patients 18 years of age and older with inadequate response to nasal corticosteroids, as add-on maintenance treatment (1.2)
- IgE-mediated food allergy in adult and pediatric patients aged 1 year and older for the reduction of allergic reactions (Type I), including anaphylaxis, that may occur with accidental exposure to one or more foods. To be used in conjunction with food allergen avoidance (1.3)
- Chronic spontaneous urticaria (CSU) in adults and adolescents 12 years of age and older who remain symptomatic despite H1 antihistamine treatment (1.4)

Limitations of Use:

- Not indicated for acute bronchospasm or status asthmaticus. (1.1, 5.3)
- Not indicated for the emergency treatment of allergic reactions, including anaphylaxis (1.3)
- Not indicated for other forms of urticaria. (1.4)

2 DOSAGE AND ADMINISTRATION

For subcutaneous (SC) administration only. (2.2, 2.3, 2.4, 2.5)

See full prescribing information for administration instructions (2.6, 2.7, 2.8).

- Asthma: XOLAIR 75 to 375 mg SC every 2 or 4 weeks. Determine dose (mg) and dosing frequency by serum total IgE level (IU/mL), measured before the start of treatment, and body weight (kg). See the dose determination charts. (2.2)
- Chronic Rhinosinusitis with Nasal Polyps: XOLAIR 75 to 600 mg SC every 2 or 4 weeks. Determine dose (mg) and dosing frequency by serum total IgE level (IU/mL), measured before the start of treatment, and body weight (kg). See the dose determination charts. (2.3)
- IgE-Mediated Food Allergy: XOLAIR 75 mg to 600 mg SC every 2 or 4 weeks. Determine dose (mg) and dosing frequency by serum total IgE level (IU/mL), measured before the start of treatment, and body weight (kg). See the dose determination chart. (2.4)
- Chronic Spontaneous Urticaria: XOLAIR 150 or 300 mg SC every 4 weeks. Dosing in CSU is not dependent on serum IgE level or body weight. (2.5)

3 DOSAGE FORMS AND STRENGTHS

- Injection: 75 mg/0.5 mL, 150 mg/mL, and 300 mg/2 mL solution in a single-dose prefilled syringe. (3)
- Injection: 75 mg/0.5 mL, 150 mg/mL and 300 mg/2 mL solution in a single-dose prefilled autoinjector. (3)
- For Injection: 150 mg lyophilized powder in a single-dose vial for reconstitution. (3)

4 CONTRAINDICATIONS

Severe hypersensitivity reaction to XOLAIR or any ingredient of XOLAIR (4, 5.1)

5 WARNINGS AND PRECAUTIONS

- Anaphylaxis: Initiate XOLAIR therapy in a healthcare setting prepared to manage anaphylaxis which can be life-threatening and observe patients for an appropriate period of time after administration. (5.1)
- Malignancy: Malignancies have been observed in clinical studies. (5.2)
- Acute Asthma Symptoms: Do not use for the treatment of acute bronchospasm or status asthmaticus. (5.3)
- Corticosteroid Reduction: Do not abruptly discontinue corticosteroids upon initiation of XOLAIR therapy. (5.4)
- Eosinophilic Conditions: Be alert to eosinophilia, vasculitic rash, worsening pulmonary symptoms, cardiac complications, and/or neuropathy, especially upon reduction of oral corticosteroids. (5.5)
- Fever, Arthralgia, and Rash: Stop XOLAIR if patients develop signs and symptoms similar to serum sickness. (5.6)
- Potential Medication Error Related to Emergency Treatment of Anaphylaxis: XOLAIR should not be used for emergency treatment of allergic reactions, including anaphylaxis. (5.9)

6 ADVERSE REACTIONS

- Asthma: The most common adverse reactions (≥ 1% of patients) in clinical studies with adult and adolescent patients ≥12 years of age were arthralgia, pain (general), leg pain, fatigue, dizziness, fracture, arm pain, pruritus, dermatitis, and earache. In clinical studies with pediatric patients 6 to <12 years of age, the most common adverse reactions (≥3% of patients) were nasopharyngitis, headache, pyrexia, upper abdominal pain, pharyngitis streptococcal, otitis media, viral gastroenteritis, arthropod bites, and epistaxis. (6.1)
- Chronic Rhinosinusitis with Nasal Polyps: The most common adverse reactions (≥ 3% of patients) in clinical studies with adult patients included the following: headache, injection site reaction, arthralgia, upper abdominal pain, and dizziness. (6.1)
- IgE-Mediated Food Allergy: The most common adverse reactions (≥3% of patients) were injection site reactions and pyrexia. (6.1)
- Chronic Spontaneous Urticaria: The most common adverse reactions (≥2% of patients) included the following: nausea, nasopharyngitis, sinusitis, upper respiratory tract infection, viral upper respiratory tract infection, arthralgia, headache, and cough. (6.1)

To report SUSPECTED ADVERSE REACTIONS, contact Genentech at 1-888-835-2555 or FDA at 1-800-FDA-1088 or www.fda.gov/medwatch.

7 DRUG INTERACTIONS

No formal drug interaction studies have been performed. (7)

FULL PRESCRIBING INFORMATION

WARNING: ANAPHYLAXIS

Anaphylaxis presenting as bronchospasm, hypotension, syncope, urticaria, and/or angioedema of the throat or tongue, has been reported to occur after administration of XOLAIR. Anaphylaxis has occurred as early as after the first dose of XOLAIR, but also has occurred beyond 1 year after beginning regularly administered treatment. Because of the risk of anaphylaxis, initiate XOLAIR therapy in a healthcare setting and closely observe patients for an appropriate period of time after XOLAIR administration. Health care providers administering XOLAIR should be prepared to manage anaphylaxis which can be life-threatening. Inform patients of the signs and symptoms of anaphylaxis and instruct them to seek immediate medical care should symptoms occur. Selection of patients for self-administration of XOLAIR should be based on criteria to mitigate risk from anaphylaxis [see Dosage and Administration (2.6), Warnings and Precautions (5.1) and Adverse Reactions (6.1, 6.2)].

1 INDICATIONS AND USAGE

1.1 Asthma

XOLAIR is indicated for adults and pediatric patients 6 years of age and older with moderate to severe persistent asthma who have a positive skin test or in vitro reactivity to a perennial aeroallergen and whose symptoms are inadequately controlled with inhaled corticosteroids.

Limitations of Use:

XOLAIR is not indicated for the relief of acute bronchospasm or status asthmaticus.

1.2 Chronic Rhinosinusitis with Nasal Polyps

XOLAIR is indicated for add-on maintenance treatment of chronic rhinosinusitis with nasal polyps (CRSwNP) in adult patients 18 years of age and older with inadequate response to nasal corticosteroids.

1.3 IgE-Mediated Food Allergy

XOLAIR is indicated for the reduction of allergic reactions (Type I), including anaphylaxis, that may occur with accidental exposure to one or more foods in adult and pediatric patients aged 1 year and older with IgE-mediated food allergy.

XOLAIR is to be used in conjunction with food allergen avoidance.

Limitations of Use:

XOLAIR is not indicated for the emergency treatment of allergic reactions, including anaphylaxis.

1.4 Chronic Spontaneous Urticaria

XOLAIR is indicated for the treatment of adults and adolescents 12 years of age and older with chronic spontaneous urticaria (CSU) who remain symptomatic despite H1 antihistamine treatment.

Limitations of Use:

XOLAIR is not indicated for treatment of other forms of urticaria.

2 DOSAGE AND ADMINISTRATION

2.1 Overview of Dosage Determination

Asthma, and Chronic Rhinosinusitis with Nasal Polyps, and IgE-Mediated Food Allergy

- Determine dosage of XOLAIR by serum total IgE level (IU/mL) measured before the start of treatment, and by body weight (kg).
- For patients with asthma, chronic rhinosinusitis with nasal polyps (CRSwNP), and IgE-mediated food allergy, dosage determination should be based on the primary diagnosis for which XOLAIR is being prescribed.
- Adjust doses for significant changes in body weight during treatment.
- Refer to Tables 1 and 2 for the recommended dosage for treatment of asthma, Table 3 for treatment of CRSwNP, and Table 4 for treatment of IgE-mediated food allergy.
- Total IgE levels are elevated during treatment and remain elevated for up to one year after the discontinuation of treatment. Therefore, re-testing of IgE levels during XOLAIR treatment cannot be used as a guide for dose determination.
  - Interruptions lasting less than one year: Dose based on serum IgE levels obtained at the initial dose determination.
  - Interruptions lasting one year or more: Re-test total serum IgE levels for dose determination (Table 1 or 2 for treatment of asthma, based on the patient's age, Table 3 for treatment of CRSwNP, and Table 4 for treatment of IgE-mediated food allergy).

Chronic Spontaneous Urticaria

Dosage of XOLAIR in patients with chronic spontaneous urticaria (CSU) is not dependent on serum IgE (free or total) level or body weight [see Dosage and Administration (2.5)].

2.2 Recommended Dosage for Asthma

The recommended dosage for asthma is XOLAIR 75 mg to 375 mg by subcutaneous injection every 2 or 4 weeks based on serum total IgE level (IU/mL) measured before the start of treatment and by body weight (kg) [see Dosage and Administration (2.1)].

- Adult and adolescent patients 12 years of age and older: Initiate dosing according to Table 1.
- Pediatric patients 6 to <12 years of age: Initiate dosing according to Table 2.

Table 1. Subcutaneous XOLAIR Doses Every 2 or 4 Weeks* for Patients 12 Years of Age and Older with Asthma

Table 2. Subcutaneous XOLAIR Doses Every 2 or 4 Weeks* for Pediatric Patients with Asthma Who Begin XOLAIR Between the Ages of 6 to <12 Years

Duration of Therapy

Periodically reassess the need for continued therapy based upon the patient's disease severity and level of asthma control.

2.3 Recommended Dosage for Chronic Rhinosinusitis with Nasal Polyps

The recommended dosage for chronic rhinosinusitis with nasal polyps (CRSwNP) is XOLAIR 75 mg to 600 mg by subcutaneous injection every 2 or 4 weeks based on serum total IgE level (IU/mL) measure before the start of treatment and by body weight (kg) [see Dosage and Administration (2.1)]. Refer to Table 3 for recommended dosage based on serum total IgE level and body weight for patients with CRSwNP.

Table 3. Subcutaneous XOLAIR Doses Every 2 or 4 Weeks* for Adult Patients with CRSwNP

Duration of Therapy

Periodically reassess the need for continued therapy based upon the patient's disease severity and level of symptom control.

2.4 Recommended Dosage for IgE-Mediated Food Allergy

The recommended dosage for IgE-mediated food allergy is XOLAIR 75 mg to 600 mg by subcutaneous injection every 2 or 4 weeks based on serum total IgE level (IU/mL), measured before the start of treatment, and by body weight [see Dosage and Administration (2.1)]. Refer to Table 4 for recommended dosage based on serum IgE level and body weight for patients with IgE-mediated food allergy.

Table 4. Subcutaneous XOLAIR Doses Every 2 or 4 Weeks* for Adult and Pediatric Patients 1 Year of Age and Older with IgE-Mediated Food Allergy

Duration of Therapy

The appropriate duration of therapy for IgE-mediated food allergy has not been evaluated. Periodically reassess the need for continued therapy.

2.5 Recommended Dosage for Chronic Spontaneous Urticaria

The recommended dosage for chronic spontaneous urticaria (CSU) is XOLAIR 150 mg or 300 mg by subcutaneous injection every 4 weeks.

- The 300 mg dose may be administered as one subcutaneous injection of 300 mg/2 mL or as two subcutaneous injections of 150 mg/mL.
- Dosing of XOLAIR in CSU patients is not dependent on serum IgE (free or total) level or body weight.

Duration of Therapy

The appropriate duration of therapy for CSU has not been evaluated. Periodically reassess the need for continued therapy.

2.6 Administration Overview

- Administer XOLAIR by subcutaneous injection.
- XOLAIR is intended for use under the guidance of a healthcare provider.
- Initiate therapy in a healthcare setting and once therapy has been safely established, the healthcare provider may determine whether self-administration of XOLAIR prefilled syringe or autoinjector by the patient or caregiver is appropriate, based on careful assessment of risk for anaphylaxis and mitigation strategies.

Selection of Patients for Self-Administration of XOLAIR Prefilled Syringe or Autoinjector

Healthcare providers should consider known risk factors for anaphylaxis to XOLAIR [see Warnings and Precautions (5.1)] and mitigation strategies when selecting patients for self-administration. Patient-specific factors including the following criteria should be considered:

1a) Asthma, CRSwNP and CSU: Patient should have no prior history of anaphylaxis to XOLAIR or other agents, such as foods, drugs, biologics, etc.
1b) IgE-Mediated Food Allergy: Patient should have no prior history of anaphylaxis to XOLAIR or other agents (except foods), such as drugs, biologics, etc.
2) Patient should receive at least 3 doses of XOLAIR under the guidance of a healthcare provider with no hypersensitivity reactions
3) Patient or caregiver is able to recognize symptoms of anaphylaxis
4) Patient or caregiver is able to treat anaphylaxis appropriately
5) Patient or caregiver is able to perform subcutaneous injections with XOLAIR prefilled syringe or autoinjector with proper technique according to the prescribed dosing regimen and Instructions for Use

2.7 XOLAIR Prefilled Syringe and Autoinjector

XOLAIR injection doses are available as a prefilled syringe or as an autoinjector. Instruct patients or caregivers to follow the directions provided in the "Instructions for Use" for preparation and administration of XOLAIR prefilled syringe or autoinjector [see Instructions for Use].

XOLAIR Prefilled Syringe

- Adolescents 12 years of age and older: XOLAIR prefilled syringe may be self-administered under adult supervision.
- Pediatric Patients 1 to 11 years of age: XOLAIR prefilled syringe should be administered by a caregiver.

XOLAIR Autoinjector

- Adolescents 12 years of age and older: XOLAIR autoinjector may be self-administered under adult supervision. The XOLAIR autoinjectors (all doses) are intended for use only in adults and adolescents aged 12 years and older.
- Pediatric Patients 1 to 11 years of age: The XOLAIR autoinjectors (all doses) are not intended for use in pediatric patients under 12 years of age.

Administration Instructions for Prefilled Syringe and Autoinjector

- Persons with latex allergies should not handle XOLAIR prefilled syringe because the needle cap of the XOLAIR 75 mg/0.5 mL and 150 mg/mL prefilled syringes contains a derivative of natural rubber latex which may cause allergic reactions in latex sensitive individuals [see How Supplied/Storage and Handling (16)].
- Visually inspect the contents of the prefilled syringe or autoinjector for particulate matter and discoloration prior to administration. XOLAIR prefilled syringe or autoinjector solution should be clear and colorless to pale brownish yellow. Do not use the prefilled syringe or autoinjector if the medicine is cloudy, discolored, or contains particles.
- Determine the number of prefilled syringes or autoinjectors needed for patient's dosage (see Table 5). For pediatric patients 1 to 11 years of age, consideration should be given to the number of prefilled syringe injections needed and volume to be injected relative to the patient's bodyweight.
- For patients requiring more than 1 injection to complete a full dose, administer each injection at least 1 inch apart from other injection sites.
- Administer subcutaneous injection into the thigh or abdomen, avoiding the 2-inch (5 cm) area directly around the navel. The outer area of the upper arms may be used only if the injection is being given by a caregiver or healthcare provider [see Instructions for Use]. The injection may take up to 15 seconds to administer.

Table 5. Number of XOLAIR Prefilled Syringes or Autoinjectors [The autoinjector (all doses) are not intended for use in patients under 12 years of age.] , Injections and Total Injection Volumes [This table represents the fewest number of injections for the patient, however, there are other syringe/autoinjector dosing combinations to achieve desired dose.]
XOLAIR Dose [The 75 mg, 150 mg, 225 mg, 300 mg, and 375 mg XOLAIR doses are approved for use in asthma patients. All doses in the table are approved for use in CRSwNP and IgE-mediated food allergy patients. The 150 mg and 300 mg XOLAIR doses are also approved for use in CSU patients.] | 75 mg | 150 mg | 300mg | Total Volume Injected
75 mg | 1 | 0 | 0 | 0.5 mL
150 mg | 0 | 1 | 0 | 1 mL
225 mg | 1 | 1 | 0 | 1.5 mL
300 mg | 0 | 0 | 1 | 2 mL
375 mg | 1 | 0 | 1 | 2.5 mL
450 mg | 0 | 1 | 1 | 3 mL
525 mg | 1 | 1 | 1 | 3.5 mL
600 mg | 0 | 0 | 2 | 4 mL

2.8 Preparation for Use and Injection of XOLAIR Lyophilized Powder

XOLAIR lyophilized powder should only be prepared and injected by a healthcare provider. The supplied XOLAIR lyophilized powder must be reconstituted with Sterile Water for Injection (SWFI) USP, using the following instructions:

1) Before reconstitution, determine the number of vials that will need to be reconstituted (each vial delivers 150 mg of XOLAIR in 1.2 mL) (see Table 6).

Table 6. Number of Vials, Injections and Total Injection Volumes
XOLAIR Dose [The 75 mg, 150 mg, 225 mg, 300 mg, and 375 mg XOLAIR doses are approved for use in asthma patients. All doses in the table are approved for use in CRSwNP and IgE-mediated food allergy patients. The 150 mg and 300 mg XOLAIR doses are also approved for use in CSU patients.] | Number of Vials | Number of Injections | Total Volume Injected
75 mg | 1 | 1 | 0.6 mL
150 mg | 1 | 1 | 1.2 mL
225 mg | 2 | 2 | 1.8 mL
300 mg | 2 | 2 | 2.4 mL
375 mg | 3 | 3 | 3.0 mL
450 mg | 3 | 3 | 3.6 mL
525 mg | 4 | 4 | 4.2 mL
600 mg | 4 | 4 | 4.8 mL

2) Draw 1.4 mL of SWFI, USP, into a 3 mL syringe equipped with a 1-inch, 18-gauge needle.
3) Place the vial upright on a flat surface and using standard aseptic technique, insert the needle and inject the SWFI, USP, directly onto the product.
4) Keeping the vial upright, gently swirl the upright vial for approximately 1 minute to evenly wet the powder. Do not shake.
5) Gently swirl the vial for 5 to 10 seconds approximately every 5 minutes in order to dissolve any remaining solids. The lyophilized product takes 15 to 20 minutes to dissolve. If it takes longer than 20 minutes to dissolve completely, gently swirl the vial for 5 to 10 seconds approximately every 5 minutes until there are no visible gel-like particles in the solution. Do not use if the contents of the vial do not dissolve completely by 40 minutes.
6) After reconstitution, XOLAIR solution is somewhat viscous and will appear clear or slightly opalescent. It is acceptable if there are a few small bubbles or foam around the edge of the vial; there should be no visible gel-like particles in the reconstituted solution. Do not use if foreign particles are present.
7) Invert the vial for 15 seconds in order to allow the solution to drain toward the stopper.
8) Use the XOLAIR solution within 8 hours following reconstitution when stored in the vial at 2ºC to 8ºC (36ºF to 46ºF), or within 4 hours of reconstitution when stored at room temperature. Reconstituted XOLAIR vials should be protected from sunlight.
9) Using a new 3 mL syringe equipped with a 1-inch, 18-gauge needle, insert the needle into the inverted vial. Position the needle tip at the very bottom of the solution in the vial stopper when drawing the solution into the syringe. The reconstituted product is somewhat viscous. Withdraw all of the product from the vial before expelling any air or excess solution from the syringe. Before removing the needle from the vial, pull the plunger all the way back to the end of the syringe barrel in order to remove all of the solution from the inverted vial.
10) Replace the 18-gauge needle with a 25-gauge needle for subcutaneous injection.
11) Expel air, large bubbles, and any excess solution in order to obtain a volume of 1.2 mL corresponding to a dose of 150 mg of XOLAIR. To obtain a volume of 0.6 mL corresponding to a dose of 75 mg of XOLAIR, expel air, large bubbles and discard 0.6 mL from the syringe. A thin layer of small bubbles may remain at the top of the solution in the syringe.
12) Administer XOLAIR by subcutaneous injection. The injection may take 5-10 seconds to administer because the solution is slightly viscous. Do not administer more than 150 mg (contents of one vial) per injection site. Divide doses of more than 150 mg between two or more injection sites. Choose a different injection site for each new injection at least 1 inch from the area used for other injections.

3 DOSAGE FORMS AND STRENGTHS

Injection:

- 75 mg/0.5 mL is a clear to slightly opalescent and colorless to pale brownish-yellow solution in a single-dose prefilled syringe with needle shield or single-dose prefilled autoinjector
- 150 mg/mL is a clear to slightly opalescent and colorless to pale brownish-yellow solution in a single-dose prefilled syringe with needle shield or single-dose prefilled autoinjector
- 300 mg/2 mL is a clear to slightly opalescent and colorless to pale brownish-yellow solution in a single-dose prefilled syringe with needle shield or single-dose prefilled autoinjector
- For injection: 150 mg white lyophilized powder in a single-dose vial for reconstitution

4 CONTRAINDICATIONS

XOLAIR is contraindicated in patients with severe hypersensitivity reaction to XOLAIR or any ingredient of XOLAIR [see Warnings and Precautions (5.1)].

5 WARNINGS AND PRECAUTIONS

5.1 Anaphylaxis

Anaphylaxis has been reported to occur after administration of XOLAIR in premarketing clinical trials and in postmarketing spontaneous reports [see Boxed Warning and Adverse Reactions (6.2)]. Signs and symptoms in these reported cases have included bronchospasm, hypotension, syncope, urticaria, and/or angioedema of the throat or tongue. Some of these events have been life-threatening. In premarketing clinical trials in patients with asthma, anaphylaxis was reported in 3 of 3507 (0.1%) patients. Anaphylaxis occurred with the first dose of XOLAIR in two patients and with the fourth dose in one patient. The time to onset of anaphylaxis was 90 minutes after administration in two patients and 2 hours after administration in one patient.

A case-control study in asthma patients showed that, among XOLAIR users, patients with a history of anaphylaxis to foods, medications, or other causes were at increased risk of anaphylaxis associated with XOLAIR, compared to those with no prior history of anaphylaxis [see Adverse Reactions (6.1)].

In postmarketing spontaneous reports, the frequency of anaphylaxis attributed to XOLAIR use was estimated to be at least 0.2% of patients based on an estimated exposure of about 57,300 patients from June 2003 through December 2006. Anaphylaxis has occurred as early as after the first dose of XOLAIR, but also has occurred beyond one year after beginning regularly scheduled treatment. Approximately 60% to 70% of anaphylaxis cases have been reported to occur within the first three doses of XOLAIR, with additional cases occurring sporadically beyond the third dose.

Initiate XOLAIR only in a healthcare setting equipped to manage anaphylaxis, which can be life-threatening. Observe patients closely for an appropriate period of time after administration of XOLAIR, taking into account the time to onset of anaphylaxis seen in premarketing clinical trials and postmarketing spontaneous reports [see Adverse Reactions (6.1, 6.2)]. Inform patients of the signs and symptoms of anaphylaxis, and instruct them to seek immediate medical care should signs or symptoms occur.

Once XOLAIR therapy has been established, administration of XOLAIR prefilled syringe or autoinjector outside of a healthcare setting by a patient or a caregiver may be appropriate for selected patients. Patient selection, determined by the healthcare provider in consultation with the patient, should take into account the pattern of anaphylaxis events seen in premarketing clinical trials and postmarketing spontaneous reports, as well as individual patient risk factors (e.g., prior history of anaphylaxis), ability to recognize signs and symptoms of anaphylaxis, and ability to perform subcutaneous injections with XOLAIR prefilled syringe or autoinjector with proper technique according to the prescribed dosing regimen and Instructions for Use [see Dosage and Administration (2.6), Adverse Reactions (6.1, 6.2)].

Discontinue XOLAIR in patients who experience a severe hypersensitivity reaction [see Contraindications (4)].

5.2 Malignancy

Malignant neoplasms were observed in 20 of 4127 (0.5%) XOLAIR-treated patients compared with 5 of 2236 (0.2%) control patients in clinical studies of adults and adolescents ≥12 years of age with asthma and other allergic disorders. The observed malignancies in XOLAIR-treated patients were a variety of types, with breast, non-melanoma skin, prostate, melanoma, and parotid occurring more than once, and five other types occurring once each. The majority of patients were observed for less than 1 year. The impact of longer exposure to XOLAIR or use in patients at higher risk for malignancy (e.g., elderly, current smokers) is not known.

In a subsequent observational study of 5007 XOLAIR-treated and 2829 non-XOLAIR-treated adolescent and adult patients with moderate to severe persistent asthma and a positive skin test reaction or in vitro reactivity to a perennial aeroallergen, patients were followed for up to 5 years. In this study, the incidence rates of primary malignancies (per 1000 patient years) were similar among XOLAIR-treated (12.3) and non-XOLAIR-treated patients (13.0) [see Adverse Reactions (6.1)]. However, study limitations preclude definitively ruling out a malignancy risk with XOLAIR. Study limitations include: the observational study design, the bias introduced by allowing enrollment of patients previously exposed to XOLAIR (88%), enrollment of patients (56%) while a history of cancer or a premalignant condition were study exclusion criteria, and the high study discontinuation rate (44%).

5.3 Acute Asthma Symptoms and Deteriorating Disease

XOLAIR has not been shown to alleviate asthma exacerbations acutely. Do not use XOLAIR to treat acute bronchospasm or status asthmaticus. Patients should seek medical advice if their asthma remains uncontrolled or worsens after initiation of treatment with XOLAIR.

5.4 Corticosteroid Reduction

Do not discontinue systemic or inhaled corticosteroids abruptly upon initiation of XOLAIR therapy for asthma or CRSwNP. Decrease corticosteroids gradually under the direct supervision of a physician. In CSU patients, the use of XOLAIR in combination with corticosteroids has not been evaluated.

5.5 Eosinophilic Conditions

In rare cases, patients with asthma on therapy with XOLAIR may present with serious systemic eosinophilia sometimes presenting with clinical features of vasculitis consistent with Churg-Strauss syndrome, a condition which is often treated with systemic corticosteroid therapy. These events usually, but not always, have been associated with the reduction of oral corticosteroid therapy. Physicians should be alert to eosinophilia, vasculitic rash, worsening pulmonary symptoms, cardiac complications, and/or neuropathy presenting in their patients. A causal association between XOLAIR and these underlying conditions has not been established.

5.6 Fever, Arthralgia, and Rash

In post-approval use, some patients have experienced a constellation of signs and symptoms including arthritis/arthralgia, rash, fever, and lymphadenopathy with an onset 1 to 5 days after the first or subsequent injections of XOLAIR. These signs and symptoms have recurred after additional doses in some patients. Although circulating immune complexes or a skin biopsy consistent with a Type III reaction were not seen with these cases, these signs and symptoms are similar to those seen in patients with serum sickness. Physicians should stop XOLAIR if a patient develops this constellation of signs and symptoms [see Adverse Reactions (6.2)].

5.7 Parasitic (Helminth) Infection

Monitor patients at high risk of geohelminth infection while on XOLAIR therapy. Insufficient data are available to determine the length of monitoring required for geohelminth infections after stopping XOLAIR treatment.

In a one-year clinical trial conducted in Brazil in adult and adolescent patients at high risk for geohelminthic infections (roundworm, hookworm, whipworm, threadworm), 53% (36/68) of XOLAIR-treated patients experienced an infection, as diagnosed by standard stool examination, compared to 42% (29/69) of placebo controls. The point estimate of the odds ratio for infection was 1.96, with a 95% confidence interval (0.88, 4.36) indicating that in this study a patient who had an infection was anywhere from 0.88 to 4.36 times as likely to have received XOLAIR than a patient who did not have an infection. Response to appropriate anti-geohelminth treatment of infection as measured by stool egg counts was not different between treatment groups.

5.8 Laboratory Tests

Serum total IgE levels increase following administration of XOLAIR due to formation of XOLAIR:IgE complexes [see Clinical Pharmacology (12.2)]. Elevated serum total IgE levels may persist for up to 1 year following discontinuation of XOLAIR. Do not use serum total IgE levels obtained less than 1 year following discontinuation to reassess the dosing regimen for asthma, CRSwNP or IgE-mediated food allergy patients, because these levels may not reflect steady-state free IgE levels [see Dosage and Administration (2.2, 2.3, 2.4)].

5.9 Potential Medication Error Related to Emergency Treatment of Anaphylaxis

XOLAIR should not be used for the emergency treatment of allergic reactions, including anaphylaxis. In studies to simulate use, some patients and caregivers did not understand that XOLAIR is not intended for the emergency treatment of allergic reactions, including anaphylaxis. The safety and effectiveness of XOLAIR for emergency treatment of allergic reactions, including anaphylaxis, have not been established. Instruct patients that XOLAIR is for maintenance use to reduce allergic reactions, including anaphylaxis, while avoiding food allergens.

6 ADVERSE REACTIONS

The following clinically significant adverse reactions are described elsewhere in the labeling:

- Anaphylaxis [see Boxed Warning and Warnings and Precautions (5.1)]
- Malignancies [see Warnings and Precautions (5.2)]

6.1 Clinical Trials Experience

Because clinical trials are conducted under widely varying conditions, adverse reaction rates observed in the clinical trials of a drug cannot be directly compared to rates in the clinical trials of another drug and may not reflect the rates observed in clinical practice.

Adverse Reactions from Clinical Studies in Adult and Adolescent Patients 12 Years of Age and Older with Asthma

The data described below reflect XOLAIR exposure for 2076 adult and adolescent patients ages 12 and older, including 1687 patients exposed for six months and 555 exposed for one year or more, in either placebo-controlled or other controlled asthma studies. The mean age of patients receiving XOLAIR was 42 years, with 134 patients 65 years of age or older; 60% were women, and 85% Caucasian. Patients received XOLAIR 150 mg to 375 mg every 2 or 4 weeks or, for patients assigned to control groups, standard therapy with or without a placebo.

The adverse reactions most frequently resulting in clinical intervention (e.g., discontinuation of XOLAIR, or the need for concomitant medication to treat an adverse reaction) were injection site reaction (45%), viral infections (23%), upper respiratory tract infection (20%), sinusitis (16%), headache (15%), and pharyngitis (11%). These reactions were observed at similar rates in XOLAIR-treated patients and control patients.

Table 7 shows adverse reactions from four placebo-controlled asthma trials that occurred ≥1% and more frequently in adult and adolescent patients 12 years of age and older receiving XOLAIR than in those receiving placebo. Adverse reactions were classified using preferred terms from the International Medical Nomenclature (IMN) dictionary. Injection site reactions were recorded separately from the reporting of other adverse reactions.

Table 7. Adverse Reactions ≥1% More Frequent in XOLAIR-Treated Adult or Adolescent Patients 12 years of Age and Older in Four Placebo-controlled Asthma Trials
Adverse reaction | XOLAIR n=738 | Placebo n=717
Body as a whole
Pain | 7% | 5%
Fatigue | 3% | 2%
Musculoskeletal system
Arthralgia | 8% | 6%
Fracture | 2% | 1%
Leg pain | 4% | 2%
Arm pain | 2% | 1%
Nervous system
Dizziness | 3% | 2%
Skin and appendages
Pruritus | 2% | 1%
Dermatitis | 2% | 1%
Special senses
Earache | 2% | 1%

There were no differences in the incidence of adverse reactions based on age (among patients under 65), gender or race.

Anaphylaxis Case Control Study

A retrospective case-control study investigated risk factors for anaphylaxis to XOLAIR among patients treated with XOLAIR for asthma. Cases with an adjudicated history of anaphylaxis to XOLAIR were compared to controls with no such history. The study found that a self-reported history of anaphylaxis to foods, medications or other causes was more common among patients with XOLAIR anaphylaxis (57% of 30 cases) compared to controls (23% of 88 controls) [OR 8.1, 95% CI 2.7 to 24.3]. Because this is a case-control study, the study cannot provide the incidence of anaphylaxis among XOLAIR users. From other sources, anaphylaxis to XOLAIR was observed in 0.1% of patients in clinical trials and at least 0.2% of patients based upon postmarketing reports. Approximately 60% to 70% of cases were reported to occur within the first three doses of XOLAIR, with additional cases occurring sporadically beyond the third dose. The time to onset for anaphylaxis was reported to occur within 2 hours for the majority of cases (approximately 75%) [see Warnings and Precautions (5.1), Adverse Reactions (6.2)].

Injection Site Reactions

In adults and adolescents, injection site reactions of any severity occurred at a rate of 45% in XOLAIR-treated patients compared with 43% in placebo-treated patients. The types of injection site reactions included: bruising, redness, warmth, burning, stinging, itching, hive formation, pain, indurations, mass, and inflammation.

Severe injection site reactions occurred more frequently in XOLAIR-treated patients compared with patients in the placebo group (12% versus 9%).

The majority of injection site reactions occurred within 1 hour post injection, lasted less than 8 days, and generally decreased in frequency at subsequent dosing visits.

Adverse Reactions from Clinical Studies in Pediatric Patients 6 to <12 Years of Age with Asthma

The data described below reflect XOLAIR exposure for 926 patients 6 to <12 years of age, including 583 patients exposed for six months and 292 exposed for one year or more, in either placebo-controlled or other controlled asthma studies. The mean age of pediatric patients receiving XOLAIR was 8.8 years; 69% were male, and 64% were Caucasian. Pediatric patients received XOLAIR 75 mg to 375 mg every 2 or 4 weeks or, for patients assigned to control groups, standard therapy with or without a placebo. No cases of malignancy were reported in patients treated with XOLAIR in these trials.

The most common adverse reactions occurring at ≥3% in the pediatric patients receiving XOLAIR and more frequently than in patients treated with placebo were nasopharyngitis, headache, pyrexia, upper abdominal pain, pharyngitis streptococcal, otitis media, viral gastroenteritis, arthropod bite, and epistaxis.

The adverse reactions most frequently resulting in clinical intervention (e.g., discontinuation of XOLAIR, or the need for concomitant medication to treat an adverse event) were bronchitis (0.2%), headache (0.2%) and urticaria (0.2%). These reactions were observed at similar rates in XOLAIR-treated patients and control patients.

Adverse Reactions from Clinical Studies in Adult Patients with Chronic Rhinosinusitis with Nasal Polyps

The data described below reflect XOLAIR exposure for 135 patients ≥ 18 years of age, exposed for six months in two placebo-controlled studies. The mean age of patients receiving XOLAIR was 49.7 years; 64% were male, and 94% were Caucasian. Patients received XOLAIR or placebo SC every 2 or 4 weeks, with dosage and frequency according to Table 3. All patients received background nasal mometasone therapy throughout the study. Table 8 lists the adverse reactions occurring in ≥3% of XOLAIR-treated patients and more frequently than in patients treated with placebo in chronic rhinosinusitis with nasal polyps (CRSwNP) Trials 1 and 2; results were pooled.

Table 8. Adverse Reactions Occurring in ≥3% of XOLAIR-Treated Patients and More Frequently than in Patients Treated with Placebo in CRSwNP Trials 1 and 2
Adverse reaction | XOLAIR n=135 | Placebo n=130
Gastrointestinal disorder
Upper abdominal pain | 4 (3.0%) | 1 (0.8%)
General disorders and administration site conditions
Injection site reactions [Injection site reactions terms: 'injection site reaction', 'injection related reaction' and 'injection site pain'. All injection site reactions were mild to moderate severity and none resulted in study discontinuation.] | 7 (5.2%) | 2 (1.5%)
Musculoskeletal system and connective tissue disorders
Arthralgia | 4 (3.0%) | 2 (1.5%)
Nervous system disorders
Headache | 11 (8.1%) | 7 (5.4%)
Dizziness | 4 (3.0%) | 1 (0.8%)
CRSwNP = Chronic Rhinosinusitis with Nasal Polyps.

Adverse Reactions from a Clinical Study in Patients with IgE-Mediated Food Allergy

The safety of XOLAIR in patients with IgE-mediated allergic reactions (Type I), including anaphylaxis, that may occur with accidental exposure to one or more foods, was based on data from the Food Allergy (FA) Trial, a randomized, double-blind, placebo-controlled trial in 168 patients (165 pediatric patients and 3 adults) who were allergic to peanut and at least two other foods [see Clinical Studies (14.3)]. Patients received a dosage of XOLAIR or placebo subcutaneously every 2 or 4 weeks for 16 to 20 weeks according to the recommended dosage based on IgE level (IU/mL), measured before the start of treatment, and by body weight (kg) provided in Table 4 [see Dosage and Administration (2.4)]. Safety data provided in Table 9 are from the primary analysis population of pediatric patients aged 1 year to 17 years. Safety data obtained from adults (n=3) in this trial was limited. Table 9 lists the adverse reactions occurring in ≥3% of XOLAIR-treated pediatric patients and more frequently than in patients treated with placebo in the FA trial. There were no discontinuations due to adverse reactions.

Table 9. Adverse Reactions Occurring in ≥3% of XOLAIR-Treated Pediatric Patients 1 Year of Age and Older and More Frequently than in Patients Treated with Placebo in FA Trial
Adverse Reaction | XOLAIR n=110 | Placebo n=55
General disorders and administration site conditions
Injection site reactions [Injection site reactions terms: 'injection site reaction','injection site urticaria','injection site discomfort','injection site erythema','injection site pain' and 'injection site rash'. All injection site reactions were mild to moderate severity and none resulted in study discontinuation.] | 17 (15.5%) | 6 (10.9%)
Pyrexia | 7 (6.4%) | 2 (3.6%)

Adverse Reactions from Clinical Studies in Patients with Chronic Spontaneous Urticaria

The safety of XOLAIR for the treatment of chronic spontaneous urticaria (CSU) was assessed in three placebo-controlled, multiple-dose clinical trials of 12 weeks' (CSU Trial 2) and 24 weeks' duration (CSU Trials 1 and 3). In CSU Trials 1 and 2, patients received XOLAIR 75 mg, 150 mg, or 300 mg or placebo every 4 weeks in addition to their baseline level of H1 antihistamine therapy throughout the treatment period. In CSU Trial 3 patients were randomized to XOLAIR 300 mg or placebo every 4 weeks in addition to their baseline level of H1 antihistamine therapy. The data described below reflect XOLAIR exposure for 733 patients enrolled and receiving at least one dose of XOLAIR in the three clinical trials, including 684 patients exposed for 12 weeks and 427 exposed for 24 weeks. The mean age of patients receiving XOLAIR 300 mg was 43 years, 75% were women, and 89% were white. The demographic profiles for patients receiving XOLAIR 150 mg and 75 mg were similar.

Table 10 shows adverse reactions that occurred in ≥2% of patients receiving XOLAIR (150 or 300 mg) and more frequently than those receiving placebo. Adverse reactions are pooled from CSU Trial 2 and the first 12 weeks of CSU Trials 1 and 3.

Table 10. Adverse Reactions Occurring in ≥2% in XOLAIR-Treated Patients and More Frequently than in Patients Treated with Placebo (Day 1 to Week 12) in CSU Trials
Adverse Reactions [by MedDRA (15.1) System Organ Class and Preferred Term] | CSU Trials 1, 2 and 3 Pooled
Adverse Reactions [by MedDRA (15.1) System Organ Class and Preferred Term] | 150mg (n=175) | 300mg (n=412) | Placebo (n=242)
Gastrointestinal disorders
Nausea | 2 (1.1%) | 11 (2.7%) | 6 (2.5%)
Infections and infestations
Nasopharyngitis | 16 (9.1%) | 27 (6.6%) | 17 (7.0%)
Sinusitis | 2 (1.1%) | 20 (4.9%) | 5 (2.1%)
Upper respiratory tract infection | 2 (1.1%) | 14 (3.4%) | 5 (2.1%)
Viral upper respiratory tract infection | 4 (2.3%) | 2 (0.5%) | (0.0%)
Musculoskeletal and connective tissue disorders
Arthralgia | 5 (2.9%) | 12 (2.9%) | 1 (0.4%)
Nervous system disorders
Headache | 21 (12.0%) | 25 (6.1%) | 7 (2.9%)
Respiratory, thoracic, and mediastinal disorders
Cough | 2 (1.1%) | 9 (2.2%) | 3 (1.2%)

Additional reactions reported during the 24-week treatment period in CSU Trials 1 and 3 [≥2% of patients receiving XOLAIR (150 mg or 300 mg) and more frequently than those receiving placebo] included: toothache, fungal infection, urinary tract infection, myalgia, pain in extremity, musculoskeletal pain, peripheral edema, pyrexia, migraine, sinus headache, anxiety, oropharyngeal pain, asthma, urticaria, and alopecia.

Injection Site Reactions in Patients with CSU

Injection site reactions of any severity occurred during the studies in more XOLAIR-treated patients [11 patients (2.7%) at 300 mg, 1 patient (0.6%) at 150 mg] compared with 2 placebo-treated patients (0.8%). The types of injection site reactions included: swelling, erythema, pain, bruising, itching, bleeding, and urticaria. None of the events resulted in study discontinuation or treatment interruption.

Cardiovascular and Cerebrovascular Events from Clinical Studies in Patients with Asthma

A 5-year observational cohort study was conducted in patients ≥12 years of age with moderate to severe persistent asthma and a positive skin test reaction to a perennial aeroallergen to evaluate the long-term safety of XOLAIR, including the risk of malignancy [see Warnings and Precautions (5.2)]. A total of 5007 XOLAIR-treated and 2829 non–XOLAIR-treated patients enrolled in the study. Similar percentages of patients in both cohorts were current (5%) or former smokers (29%). Patients had a mean age of 45 years and were followed for a mean of 3.7 years. More XOLAIR-treated patients were diagnosed with severe asthma (50%) compared to the non–XOLAIR-treated patients (23%) and 44% of patients prematurely discontinued the study. Additionally, 88% of patients in the XOLAIR-treated cohort had been previously exposed to XOLAIR for a mean of 8 months.

A higher incidence rate (per 1000 patient-years) of overall cardiovascular and cerebrovascular serious adverse events (SAEs) was observed in XOLAIR-treated patients (13.4) compared to non–XOLAIR-treated patients (8.1). Increases in rates were observed for transient ischemic attack (0.7 versus 0.1), myocardial infarction (2.1 versus 0.8), pulmonary hypertension (0.5 versus 0), pulmonary embolism/venous thrombosis (3.2 versus 1.5), and unstable angina (2.2 versus 1.4), while the rates observed for ischemic stroke and cardiovascular death were similar among both study cohorts. The results suggest a potential increased risk of serious cardiovascular and cerebrovascular events in patients treated with XOLAIR. However, the observational study design, the inclusion of patients previously exposed to XOLAIR (88%), baseline imbalances in cardiovascular risk factors between the treatment groups, an inability to adjust for unmeasured risk factors, and the high study discontinuation rate limit the ability to quantify the magnitude of the risk.

A pooled analysis of 25 randomized double-blind, placebo-controlled clinical trials of 8 to 52 weeks in duration was conducted to further evaluate the imbalance in cardiovascular and cerebrovascular SAEs noted in the above observational cohort study. A total of 3342 XOLAIR-treated patients and 2895 placebo-treated patients were included in the pooled analysis. The patients had a mean age of 38 years, and were followed for a mean duration of 6.8 months. No notable imbalances were observed in the rates of cardiovascular and cerebrovascular SAEs listed above. However, the results of the pooled analysis were based on a low number of events, slightly younger patients, and shorter duration of follow-up than the observational cohort study; therefore, the results are insufficient to confirm or reject the findings noted in the observational cohort study.

Adverse Reactions from Clinical Study in Healthy Adults

Injection Site Reactions in Healthy Adults

In an open label trial in healthy adults, in which the 300 mg/2 mL autoinjector was compared to the 300 mg/2 mL prefilled syringe, injection site reactions (e.g., induration, pain, erythema, hemorrhage, swelling, discomfort, bruising, hypoesthesia, edema, pruritus) were observed in 24% (16/66) of subjects treated with the autoinjector compared with 14% (9/64) of subjects treated with the prefilled syringe.

6.2 Postmarketing Experience

The following adverse reactions have been identified during postapproval use of XOLAIR. Because these reactions are reported voluntarily from a population of uncertain size, it is not always possible to reliably estimate their frequency or establish a causal relationship to drug exposure.

Anaphylaxis: Based on spontaneous reports and an estimated exposure of about 57,300 patients from June 2003 through December 2006, the frequency of anaphylaxis attributed to XOLAIR use was estimated to be at least 0.2% of patients.

Diagnostic criteria of anaphylaxis were skin or mucosal tissue involvement, and, either airway compromise, and/or reduced blood pressure with or without associated symptoms, and a temporal relationship to XOLAIR administration with no other identifiable cause. Signs and symptoms in these reported cases included bronchospasm, hypotension, syncope, urticaria, angioedema of the throat or tongue, dyspnea, cough, chest tightness, and/or cutaneous angioedema. Pulmonary involvement was reported in 89% of the cases. Hypotension or syncope was reported in 14% of cases. Fifteen percent of the reported cases resulted in hospitalization. A previous history of anaphylaxis unrelated to XOLAIR was reported in 24% of the cases.

Of the reported cases of anaphylaxis attributed to XOLAIR, 39% occurred with the first dose, 19% occurred with the second dose, 10% occurred with the third dose, and the rest after subsequent doses. One case occurred after 39 doses (after 19 months of continuous therapy, anaphylaxis occurred when treatment was restarted following a 3-month gap). The time to onset of anaphylaxis in these cases was up to 30 minutes in 35%, greater than 30 and up to 60 minutes in 16%, greater than 60 and up to 90 minutes in 2%, greater than 90 and up to 120 minutes in 6%, greater than 2 hours and up to 6 hours in 5%, greater than 6 hours and up to 12 hours in 14%, greater than 12 hours and up to 24 hours in 8%, and greater than 24 hours and up to 4 days in 5%. In 9% of cases the times to onset were unknown.

Twenty-three patients who experienced anaphylaxis were rechallenged with XOLAIR and 18 patients had a recurrence of similar symptoms of anaphylaxis. In addition, anaphylaxis occurred upon rechallenge with XOLAIR in 4 patients who previously experienced urticaria only.

Eosinophilic Conditions: Eosinophilic conditions have been reported [see Warnings and Precautions (5.5)].

Fever, Arthralgia, and Rash: A constellation of signs and symptoms including arthritis/arthralgia, rash (urticaria or other forms), fever and lymphadenopathy similar to serum sickness have been reported in post-approval use of XOLAIR [see Warnings and Precautions (5.6)].

Hematologic: Severe thrombocytopenia has been reported.

Skin: Hair loss has been reported.

7 DRUG INTERACTIONS

No formal drug interaction studies have been performed with XOLAIR.

In patients with asthma, CRSwNP, and IgE-mediated food allergy the concomitant use of XOLAIR and allergen immunotherapy has not been evaluated.

In patients with CSU, the use of XOLAIR in combination with immunosuppressive therapies has not been studied.

8 USE IN SPECIFIC POPULATIONS

8.1 Pregnancy

Risk Summary

A registry study of XOLAIR exposure during pregnancy showed no increase in the rate of major birth defects or miscarriage. There was an increased rate of low birth weight among registry infants compared to infants in the other cohorts, despite average gestational age at birth; however, women taking XOLAIR during pregnancy also had more severe asthma, which makes it difficult to determine whether the low birth weight is due to the drug or the disease severity [see Data]. There are risks associated with poorly or moderately controlled asthma in pregnancy [see Clinical Considerations].

Human IgG antibodies are known to cross the placental barrier; therefore, XOLAIR may be transmitted from the mother to the developing fetus.

In animal reproduction studies, no evidence of fetal harm was observed in Cynomolgus monkeys with subcutaneous doses of omalizumab up to approximately 5 times the maximum recommended human dose (MRHD) [see Data].

The estimated background risk of major birth defects and miscarriage for the indicated population(s) is unknown. All pregnancies have a background risk of birth defect, loss, or other adverse outcomes. In the US general population, the estimated background risk of major birth defects and miscarriage in clinically recognized pregnancies is 2% to 4% and 15% to 20%, respectively.

Clinical Considerations

Disease-associated maternal and/or embryo/fetal risk

In women with poorly or moderately controlled asthma, evidence demonstrates that there is an increased risk of preeclampsia in the mother and prematurity, low birth weight, and small for gestational age in the neonate. The level of asthma control should be closely monitored in pregnant women and treatment adjusted as necessary to maintain optimal control.

Data

Human Data

A prospective cohort pregnancy exposure registry study conducted in the US from 2006 to 2018, included 250 pregnant women with asthma treated with XOLAIR. Of these, 246 patients were exposed to XOLAIR in the first trimester of pregnancy, and the median exposure duration was 8.7 months.

The registry findings for applicable mother and infant subgroups were compared to age-adjusted frequencies in a disease-matched external cohort of 1,153 pregnant women with asthma (without exposure to XOLAIR) identified from healthcare databases of residents in the Canadian province of Quebec, and referred to as the Quebec External Comparator Cohort ("comparator cohort").

Among applicable registry infants, the prevalence of major congenital anomalies (8.1%) was similar to that for infants in the comparator cohort (8.9%). Among applicable registry pregnancies, 99.1% led to live births, similar to 99.3% for the comparator cohort. There was an increased rate of low birth weight among registry infants (13.7%) as compared to the comparator cohort (9.8%); however, women taking XOLAIR during pregnancy also had more severe asthma, which makes it difficult to determine whether the low birth weight is due to the drug or the disease severity.

The registry study cannot definitively establish the absence of any risk because of methodological limitations, including the observational nature of the registry, small sample size, and potential differences between the registry population and the comparator cohort.

Animal Data

Reproductive studies have been performed in Cynomolgus monkeys. There was no evidence of maternal toxicity, embryotoxicity, or teratogenicity when omalizumab was administered throughout the period of organogenesis at doses that produced exposures approximately 5 times the MRHD (on a mg/kg basis with maternal subcutaneous doses up to 75 mg/kg/week). Omalizumab did not elicit adverse effects on fetal or neonatal growth when administered throughout late gestation, delivery, and nursing.

8.2 Lactation

Risk Summary

There is no information regarding the presence of omalizumab in human milk, or the effects on milk production. However, omalizumab is a human monoclonal antibody (IgG1 kappa), and immunoglobulin (IgG) is present in human milk in small amounts.

The majority of infants (80.9%, 186/230) in the pregnancy exposure registry were breastfed. Events categorized as "infections and infestations" were not significantly increased in infants who were exposed to XOLAIR through breastfeeding compared with infants who were not breastfed, or infants who were breastfed without exposure to XOLAIR.

The developmental and health benefits of breastfeeding should be considered along with the mother's clinical need for XOLAIR and any potential adverse effects on the breastfed child from omalizumab or from the underlying maternal condition.

8.4 Pediatric Use

Asthma

Safety and effectiveness of XOLAIR for moderate to severe persistent asthma who had a positive skin test or in vitro reactivity to a perennial aeroallergen and whose symptoms are inadequately controlled with inhaled corticosteroids, have been established in pediatric patients aged 6 years and older. Use of XOLAIR for this indication is supported by evidence from adequate and well-controlled studies. XOLAIR was evaluated in 2 trials in 926 (XOLAIR 624; placebo 302) pediatric patients 6 to <12 years of age with moderate to severe persistent asthma who had a positive skin test or in vitro reactivity to a perennial aeroallergen. One trial was a pivotal trial of similar design and conduct to that of adult and adolescent Asthma Trials 1 and 2. The other trial was primarily a safety study and included evaluation of efficacy as a secondary outcome. In the pivotal trial, XOLAIR-treated patients had a statistically significant reduction in the rate of exacerbations (exacerbation was defined as worsening of asthma that required treatment with systemic corticosteroids or a doubling of the baseline ICS dose) [see Clinical Studies (14.1)].

Safety and efficacy in pediatric patients with asthma below 6 years of age have not been established.

Chronic Rhinosinusitis with Nasal Polyps

Safety and effectiveness in pediatric patients with chronic rhinosinusitis with nasal polyps (CRSwNP) below 18 years of age have not been established.

IgE-Mediated Food Allergy

The safety and effectiveness of XOLAIR for the reduction of allergic reactions (Type I), including anaphylaxis, that may occur with accidental exposure to one or more foods have been established in pediatric patients aged 1 year and older with IgE-mediated food allergy. Use of XOLAIR for this indication is supported by evidence from an adequate and well-controlled study that included a total of 165 pediatric patients; 61 patients aged 1 year to less than 6 years of age and 104 patients aged 6 to less than 18 years of age. A significantly greater percentage of XOLAIR-treated patients compared to placebo-treated patients was able to consume a single dose of food (peanut, cashew, milk, egg) without dose- limiting symptoms [see Clinical Studies (14.3)].

Safety and effectiveness in pediatric patients with IgE-mediated food allergy below 1 year of age have not been established.

Chronic Spontaneous Urticaria

The safety and effectiveness of XOLAIR for chronic spontaneous urticaria (CSU) who remain symptomatic despite H1 antihistamine treatment have been established in pediatric patients aged 12 years and older. Use of XOLAIR in this population is supported by evidence from adequate and well-controlled studies. Adolescent patients with CSU were evaluated in 39 patients 12 to 17 years of age (XOLAIR 29, placebo 10) included in three randomized, placebo-controlled CSU trials. A numerical decrease in weekly itch score was observed, and adverse reactions were similar to those reported in patients 18 years and older.

Safety and effectiveness in pediatric patients with CSU below 12 years of age have not been established.

8.5 Geriatric Use

In clinical studies, 134 asthma patients, 20 CRSwNP patients, 37 CSU patients and no IgE-mediated food allergy patients 65 years of age or older were treated with XOLAIR. Although there were no apparent age-related differences observed in these studies, the number of patients aged 65 and over is not sufficient to determine whether they respond differently from younger patients.

11 DESCRIPTION

Omalizumab is a recombinant DNA-derived humanized IgG1κ monoclonal antibody that selectively binds to human immunoglobulin E (IgE). The antibody has a molecular weight of approximately 149 kiloDaltons. XOLAIR is produced by a Chinese hamster ovary cell suspension culture.

XOLAIR (omalizumab) is administered as a subcutaneous (SC) injection and is available in prefilled syringe, autoinjector and in vials.

XOLAIR Injection (Prefilled Syringe or Autoinjector)

XOLAIR (omalizumab) injection is supplied as a sterile, preservative-free, clear to slightly opalescent and colorless to pale brownish-yellow solution for subcutaneous injection. XOLAIR (omalizumab) injection is available as a single-dose prefilled syringe or a single-dose autoinjector.

Each 75 mg prefilled syringe or autoinjector delivers 75 mg omalizumab in 0.5 mL and contains arginine hydrochloride (21.05 mg), histidine (0.68 mg), L-histidine hydrochloride monohydrate (1.17 mg), and polysorbate 20 (0.2 mg) in Sterile Water for Injection (SWFI), USP.

Each 150 mg prefilled syringe or autoinjector delivers 150 mg omalizumab in 1 mL and contains arginine hydrochloride (42.1 mg), histidine (1.37 mg), L-histidine hydrochloride monohydrate (2.34 mg), and polysorbate 20 (0.4 mg) in SWFI, USP.

Each 300 mg prefilled syringe or autoinjector delivers 300 mg omalizumab in 2 mL and contains arginine hydrochloride (84.2 mg), histidine (2.74 mg), L-histidine hydrochloride monohydrate (4.68 mg), and polysorbate 20 (0.8 mg) in SWFI, USP.

The needle cap of the XOLAIR 75 mg/0.5 mL and 150 mg/mL prefilled syringe with 26-gauge staked needle contains a derivative of natural rubber latex which may cause allergic reactions in latex sensitive individuals [see How Supplied/Storage and Handling (16)].

The XOLAIR autoinjector is not made with natural rubber latex.

XOLAIR for Injection (Vial)

XOLAIR (omalizumab) for injection is a sterile, white, preservative free, lyophilized powder in a single-dose vial. After reconstitution with 1.4 mL of Sterile Water for Injection, USP, the vial contains 150 mg of omalizumab per 1.2 mL of reconstituted solution for subcutaneous injection. Each 1.2 mL of reconstituted solution also contains histidine (1.3 mg), L-histidine hydrochloride monohydrate (2.1 mg), polysorbate 20 (0.4 mg) and sucrose (108 mg).

12 CLINICAL PHARMACOLOGY

12.1 Mechanism of Action

Asthma, Chronic Rhinosinusitis with Nasal Polyps, and IgE-Mediated Food Allergy

Omalizumab inhibits the binding of IgE to the high-affinity IgE receptor (FcεRI) on the surface of mast cells, basophils, and dendritic cells, resulting in FcεRI down-regulation on these cells.

In allergic asthmatics, treatment with omalizumab inhibits IgE-mediated inflammation, as evidenced by reduced blood and tissue eosinophils and reduced inflammatory mediators, including IL-4, IL-5, and IL-13.

Chronic Spontaneous Urticaria

Omalizumab binds to IgE and lowers free IgE levels. Subsequently, IgE receptors (FcεRI) on cells down-regulate. The mechanism by which these effects of omalizumab result in an improvement of chronic spontaneous urticaria (CSU) symptoms is unknown.

12.2 Pharmacodynamics

Asthma

In clinical studies, serum free IgE levels were reduced in a dose-dependent manner within 1 hour following the first dose and maintained between doses. Mean serum free IgE decrease was greater than 96% using recommended doses. Serum total IgE levels (i.e., bound and unbound) increased after the first dose due to the formation of omalizumab:IgE complexes, which have a slower elimination rate compared with free IgE. At 16 weeks after the first dose, average serum total IgE levels were five-fold higher compared with pre-treatment when using standard assays. After discontinuation of XOLAIR dosing, the XOLAIR-induced increase in total IgE and decrease in free IgE were reversible, with no observed rebound in IgE levels after drug washout. Total IgE levels did not return to pre-treatment levels for up to one year after discontinuation of XOLAIR.

Chronic Rhinosinusitis with Nasal Polyps

In clinical studies in chronic rhinosinusitis with nasal polyps (CRSwNP) patients, omalizumab treatment led to a reduction in serum free IgE and an increase in serum total IgE levels, similar to the observations in asthma patients. The mean total IgE concentrations at baseline were 168 IU/mL and 218 IU/mL in CRSwNP Trial 1 and 2, respectively. After repeated dosing every 2 or 4 weeks, with dosage and frequency according to Table 3, the mean predose free IgE concentrations at Week 16 were 10.0 IU/mL in CRSwNP Trial 1 and 11.7 IU/mL in CRSwNP Trial 2 and remained stable at 24 weeks of treatment. Total IgE levels in serum increased due to the formation of omalizumab-IgE complexes, which have a slower elimination rate compared with free IgE. After repeated dosing every 2 or 4 weeks, with dosage and frequency according to Table 3, mean and median predose serum total IgE levels at Week 16 were 3- to 4- fold higher compared with pre-treatment levels, and remained stable between 16 and 24 weeks of treatment.

IgE-Mediated Food Allergy

In a clinical study in patients with IgE-mediated food allergy, omalizumab treatment led to a reduction in serum free IgE and an increase in serum total IgE levels, similar to the observations in asthma patients. The mean total IgE concentration at baseline was 810 IU/mL. After repeated dosing every 2 or 4 weeks, with dosage and frequency according to Table 4, the mean pre-dose free IgE concentration at Week 16 was 10.0 IU/mL. Mean total IgE levels in serum increased about 2.4-fold due to the formation of omalizumab-IgE complexes, which have a longer half-life compared with free IgE.

Chronic Spontaneous Urticaria

In clinical studies in chronic spontaneous urticaria (CSU) patients, XOLAIR treatment led to a dose-dependent reduction of serum free IgE and an increase of serum total IgE levels, similar to the observations in asthma patients. Maximum suppression of free IgE was observed 3 days following the first subcutaneous dose. After repeat dosing once every 4 weeks, predose serum free IgE levels remained stable between 12 and 24 weeks of treatment. Total IgE levels in serum increased after the first dose due to the formation of omalizumab-IgE complexes which have a slower elimination rate compared with free IgE. After repeat dosing once every 4 weeks at 75 mg up to 300 mg, average predose serum total IgE levels at Week 12 were two- to three-fold higher compared with pre-treatment levels, and remained stable between 12 and 24 weeks of treatment. After discontinuation of XOLAIR dosing, free IgE levels increased and total IgE levels decreased towards pre-treatment levels over a 16-week follow-up period.

12.3 Pharmacokinetics

After SC administration, omalizumab was absorbed with an average absolute bioavailability of 62%. Following a single SC dose in adult and adolescent patients with asthma, omalizumab was absorbed slowly, reaching peak serum concentrations after an average of 7–8 days. In patients with CSU, the peak serum concentration was reached at a similar time after a single SC dose. The pharmacokinetics of omalizumab was linear at doses greater than 0.5 mg/kg. In patients with asthma, following multiple doses of XOLAIR, areas under the serum concentration-time curve from Day 0 to Day 14 at steady state were up to 6-fold of those after the first dose. In patients with CSU, omalizumab exhibited linear pharmacokinetics across the dose range of 75 mg to 600 mg given as single subcutaneous dose. Following repeat dosing from 75 to 300 mg every 4 weeks, trough serum concentrations of omalizumab increased proportionally with the dose levels.

In vitro, omalizumab formed complexes of limited size with IgE. Precipitating complexes and complexes larger than 1 million daltons in molecular weight were not observed in vitro or in vivo. Tissue distribution studies in Cynomolgus monkeys showed no specific uptake of ^125I-omalizumab by any organ or tissue. The apparent volume of distribution of omalizumab in patients with asthma following SC administration was 78 ± 32 mL/kg. In patients with CSU, based on population pharmacokinetics, distribution of omalizumab was similar to that in patients with asthma.

Clearance of omalizumab involved IgG clearance processes as well as clearance via specific binding and complex formation with its target ligand, IgE. Liver elimination of IgG included degradation in the liver reticuloendothelial system (RES) and endothelial cells. Intact IgG was also excreted in bile. In studies with mice and monkeys, omalizumab:IgE complexes were eliminated by interactions with Fcγ receptors within the RES at rates that were generally faster than IgG clearance. In asthma patients omalizumab serum elimination half-life averaged 26 days, with apparent clearance averaging 2.4 ± 1.1 mL/kg/day. Doubling body weight approximately doubled apparent clearance. In CSU patients, at steady state, based on population pharmacokinetics, omalizumab serum elimination half-life averaged 24 days and apparent clearance averaged 240 mL/day (corresponding to 3.0 mL/kg/day for an 80 kg patient).

Specific Populations

Asthma

The population pharmacokinetics of omalizumab was analyzed to evaluate the effects of demographic characteristics in patients with asthma. Analyses of these data suggested that no dose adjustments are necessary for age (6 to 76 years), race, ethnicity, or gender.

Chronic Rhinosinusitis with Nasal Polyps

The population pharmacokinetics analyses of omalizumab suggested that the pharmacokinetics of omalizumab in chronic rhinosinusitis with nasal polyps (CRSwNP) were consistent with that in asthma. Graphical covariate analyses were performed to evaluate the effects of demographic characteristics and other factors on omalizumab exposure and clinical responses. These analyses demonstrate that no dose adjustments are necessary for age (18 to 75 years) or gender. Race and ethnicity data are too limited in CRSwNP studies to inform dose adjustment.

IgE-Mediated Food Allergy

Population pharmacokinetic (PK) analyses of omalizumab suggested that the PK of omalizumab in patients with IgE-mediated food allergy were generally consistent with that in patients with asthma. Covariate analyses were performed to evaluate the effects of demographic characteristics and other factors on omalizumab exposure and clinical responses. These analyses demonstrate that no dose adjustments are necessary for age (1 year and older), race, ethnicity, or gender.

Chronic Spontaneous Urticaria

The population pharmacokinetics of omalizumab was analyzed to evaluate the effects of demographic characteristics and other factors on omalizumab exposure in patients with chronic spontaneous urticaria (CSU). Covariate effects were evaluated by analyzing the relationship between omalizumab concentrations and clinical responses. These analyses demonstrate that no dose adjustments are necessary for age (12 to 75 years), race/ethnicity, gender, body weight, body mass index, or baseline IgE level.

12.6 Immunogenicity

The observed incidence of anti-drug antibodies is highly dependent on the sensitivity and specificity of the assay. Differences in assay methods preclude meaningful comparisons of the incidence of anti-drug antibodies in the studies described below with the incidence of anti-drug antibodies in other studies, including those of XOLAIR or of other omalizumab products.

Antibodies to XOLAIR were detected in approximately 1/1723 (<0.1%) of patients treated with XOLAIR in the clinical studies evaluated for asthma in patients 12 years of age and older. In three pediatric studies, antibodies to XOLAIR were detected in one patient out of 581 patients 6 to <12 years of age treated with XOLAIR and evaluated for antibodies. There were no detectable antibodies in the patients treated in the CSU clinical trials, but due to levels of XOLAIR at the time of anti-therapeutic antibody sampling and missing samples for some patients, antibodies to XOLAIR could only have been determined in 88% of the 733 patients treated in these clinical studies. The data reflect the percentage of patients whose test results were considered positive for antibodies to XOLAIR in ELISA assays and are highly dependent on the sensitivity and specificity of the assays.

Anti-drug antibodies were not measured in the CRSwNP or IgE-mediated food allergy trials.

13 NONCLINICAL TOXICOLOGY

13.1 Carcinogenesis, Mutagenesis, Impairment of Fertility

No long-term studies have been performed in animals to evaluate the carcinogenic potential of XOLAIR.

There were no effects on fertility and reproductive performance in male and female Cynomolgus monkeys that received XOLAIR at subcutaneous doses up to 75 mg/kg/week (approximately 5 times the maximum recommended human dose on a mg/kg basis).

14 CLINICAL STUDIES

14.1 Asthma

Adult and Adolescent Patients 12 Years of Age and Older

The safety and efficacy of XOLAIR were evaluated in three randomized, double-blind, placebo-controlled, multicenter trials.

The trials enrolled patients 12 to 76 years old, with moderate to severe persistent (NHLBI criteria) asthma for at least one year, and a positive skin test reaction to a perennial aeroallergen. In all trials, XOLAIR dosing was based on body weight and baseline serum total IgE concentration. All patients were required to have a baseline IgE between 30 and 700 IU/mL and body weight not more than 150 kg. Patients were treated according to a dosing table to administer at least 0.016 mg/kg/IU (IgE/mL) of XOLAIR or a matching volume of placebo over each 4-week period. The maximum XOLAIR dose per 4 weeks was 750 mg.

In all three trials an exacerbation was defined as a worsening of asthma that required treatment with systemic corticosteroids or a doubling of the baseline ICS dose. Most exacerbations were managed in the outpatient setting and the majority were treated with systemic steroids. Hospitalization rates were not significantly different between XOLAIR and placebo-treated patients; however, the overall hospitalization rate was small. Among those patients who experienced an exacerbation, the distribution of exacerbation severity was similar between treatment groups.

Asthma Trials 1 and 2

At screening, patients in Asthma Trials 1 and 2 had a forced expiratory volume in one second (FEV1) between 40% and 80% predicted. All patients had a FEV1 improvement of at least 12% following beta2-agonist administration. All patients were symptomatic and were being treated with inhaled corticosteroids (ICS) and short-acting beta2-agonists. Patients receiving other concomitant controller medications were excluded, and initiation of additional controller medications while on study was prohibited. Patients currently smoking were excluded.

Each trial was comprised of a run-in period to achieve a stable conversion to a common ICS (beclomethasone dipropionate), followed by randomization to XOLAIR or placebo. Patients received XOLAIR for 16 weeks with an unchanged corticosteroid dose unless an acute exacerbation necessitated an increase. Patients then entered an ICS reduction phase of 12 weeks during which ICS dose reduction was attempted in a step-wise manner.

The distribution of the number of asthma exacerbations per patient in each group during a study was analyzed separately for the stable steroid and steroid-reduction periods.

In both Asthma Trials 1 and 2 the number of exacerbations per patient was reduced in patients treated with XOLAIR compared with placebo (Table 11).

Measures of airflow (FEV1) and asthma symptoms were also evaluated in these trials. The clinical relevance of the treatment-associated differences is unknown. Results from the stable steroid phase Asthma Trial 1 are shown in Table 12. Results from the stable steroid phase of Asthma Trial 2 and the steroid reduction phases of both Asthma Trials 1 and 2 were similar to those presented in Table 12.

Table 11. Frequency of Asthma Exacerbations per Patient by Phase in Asthma Trials 1 and 2
 | Stable Steroid Phase (16 wks)
 | Asthma Trial 1 |  | Asthma Trial 2
Exacerbations per patient | XOLAIR N=268 | Placebo N=257 | XOLAIR N=274 | Placebo N=272
0 | 85.8% | 76.7% | 87.6% | 69.9%
1 | 11.9% | 16.7% | 11.3% | 25.0%
≥2 | 2.2% | 6.6% | 1.1% | 5.1%
p-Value | 0.005 |  | <0.001
Mean number exacerbations/patient | 0.2 | 0.3 | 0.1 | 0.4
 | Steroid Reduction Phase (12 wks)
Exacerbations per patient | XOLAIR N=268 | Placebo N=257 | XOLAIR N=274 | Placebo N=272
0 | 78.7% | 67.7% | 83.9% | 70.2%
1 | 19.0% | 28.4% | 14.2% | 26.1%
≥2 | 2.2% | 3.9% | 1.8% | 3.7%
p-Value | 0.004 |  | <0.001
Mean number exacerbations/patient | 0.2 | 0.4 | 0.2 | 0.3

Table 12. Asthma Symptoms and Pulmonary Function During Stable Steroid Phase of Asthma Trial 1
 | XOLAIR N=268 [Number of patients available for analysis ranges 255-258 in the XOLAIR group and 238-239 in the placebo group.] |  | Placebo N=257
Endpoint | Mean Baseline | Median Change (Baseline to Wk 16) | Mean Baseline | Median Change (Baseline to Wk 16)
Total asthma symptom score | 4.3 | –1.5 [Comparison of XOLAIR versus placebo (p < 0.05).] | 4.2 | –1.1
Nocturnal asthma score | 1.2 | –0.4 | 1.1 | –0.2
Daytime asthma score | 2.3 | –0.9 | 2.3 | –0.6
FEV1 % predicted | 68 | 3 | 68 | 0
Asthma symptom scale: total score from 0 (least) to 9 (most); nocturnal and daytime scores from 0 (least) to 4 (most symptoms).

Asthma Trial 3

In Asthma Trial 3, there was no restriction on screening FEV1, and unlike Asthma Trials 1 and 2, long-acting beta2-agonists were allowed. Patients were receiving at least 1000 µg/day fluticasone propionate and a subset was also receiving oral corticosteroids. Patients receiving other concomitant controller medications were excluded, and initiation of additional controller medications while on study was prohibited. Patients currently smoking were excluded.

The trial was comprised of a run-in period to achieve a stable conversion to a common ICS (fluticasone propionate), followed by randomization to XOLAIR or placebo. Patients were stratified by use of ICS-only or ICS with concomitant use of oral steroids. Patients received XOLAIR for 16 weeks with an unchanged corticosteroid dose unless an acute exacerbation necessitated an increase. Patients then entered an ICS reduction phase of 16 weeks during which ICS or oral steroid dose reduction was attempted in a step-wise manner.

The number of exacerbations in patients treated with XOLAIR was similar to that in placebo-treated patients (Table 13). The absence of an observed treatment effect may be related to differences in the patient population compared with Asthma Trials 1 and 2, study sample size, or other factors.

Table 13. Percentage of Patients with Asthma Exacerbations by Subgroup and Phase in Asthma Trial 3
 | Stable Steroid Phase (16 wks)
 | Inhaled Only |  | Oral + Inhaled
 | XOLAIR N=126 | Placebo N=120 | XOLAIR N=50 | Placebo N=45
% Patients with ≥1 exacerbations | 15.9% | 15.0% | 32.0% | 22.2%
Difference (95% CI) | 0.9 (–9.7, 13.7) |  | 9.8 (–10.5, 31.4)
 | Steroid Reduction Phase (16 wks)
 | XOLAIR N=126 | Placebo N=120 | XOLAIR N=50 | Placebo N=45
% Patients with ≥1 exacerbations | 22.2% | 26.7% | 42.0% | 42.2%
Difference (95% CI) | –4.4 (–17.6, 7.4) |  | –0.2 (–22.4, 20.1)

In all three of the trials, a reduction of asthma exacerbations was not observed in the XOLAIR-treated patients who had FEV1>80% at the time of randomization. Reductions in exacerbations were not seen in patients who required oral steroids as maintenance therapy.

Pediatric Patients 6 to <12 Years of Age

The safety and efficacy of XOLAIR in pediatric patients 6 to <12 years of age with moderate to severe asthma is based on one randomized, double-blind, placebo controlled, multi-center trial (Asthma Trial 4 [NCT00079937]) and an additional supportive study (Asthma Trial 5).

Asthma Trial 4 was a 52-week study that evaluated the safety and efficacy of XOLAIR as add-on therapy in 628 pediatric patients ages 6 to <12 years with moderate to severe asthma inadequately controlled despite the use of inhaled corticosteroids (fluticasone propionate DPI ≥200 mcg/day or equivalent) with or without other controller asthma medications. Eligible patients were those with a diagnosis of asthma >1 year, a positive skin prick test to at least one perennial aeroallergen, and a history of clinical features such as daytime and/or night-time symptoms and exacerbations within the year prior to study entry. During the first 24 weeks of treatment, steroid doses remained constant from baseline. This was followed by a 28-week period during which inhaled corticosteroid adjustment was allowed.

The primary efficacy variable was the rate of asthma exacerbations during the 24-week, fixed steroid treatment phase. An asthma exacerbation was defined as a worsening of asthma symptoms as judged clinically by the investigator, requiring doubling of the baseline inhaled corticosteroid dose for at least 3 days and/or treatment with rescue systemic (oral or IV) corticosteroids for at least 3 days. At 24 weeks, the XOLAIR group had a statistically significantly lower rate of asthma exacerbations (0.45 vs. 0.64) with an estimated rate ratio of 0.69 (95% CI: 0.53, 0.90).

The XOLAIR group also had a lower rate of asthma exacerbations compared to placebo over the full 52-week double-blind treatment period (0.78 vs. 1.36; rate ratio: 0.57; 95% CI: 0.45, 0.72). Other efficacy variables such as nocturnal symptom scores, beta-agonist use, and measures of airflow (FEV1) were not significantly different in XOLAIR-treated patients compared to placebo.

Asthma Trial 5 was a 28-week randomized, double blind, placebo-controlled study that primarily evaluated safety in 334 pediatric patients, 298 of whom were 6 to <12 years of age, with moderate to severe asthma who were well-controlled with inhaled corticosteroids (beclomethasone dipropionate 168-420 mcg/day). A 16-week steroid treatment period was followed by a 12-week steroid dose reduction period. Patients treated with XOLAIR had fewer asthma exacerbations compared to placebo during both the 16-week fixed steroid treatment period (0.18 vs. 0.32; rate ratio: 0.58; 95% CI: 0.35, 0.96) and the 28-week treatment period (0.38 vs. 0.76; rate ratio: 0.50; 95% CI: 0.36, 0.71).

14.2 Chronic Rhinosinusitis with Nasal Polyps

Adult Patients 18 Years of Age and Older

The safety and efficacy of XOLAIR was evaluated in two, randomized, multicenter, double-blind, placebo-controlled clinical trials (CRSwNP Trial 1 [NCT03280550] and CRSwNP Trial 2 [NCT03280537]) that enrolled patients with chronic rhinosinusitis with nasal polyps (CRSwNP) with inadequate response to nasal corticosteroids (CRSwNP Trial 1, n=138; CRSwNP Trial 2, n=127). Patients received XOLAIR or placebo SC every 2 or 4 weeks, with XOLAIR dosage and frequency according to Table 3, for 24 weeks followed by a 4-week follow-up period. All patients received background nasal mometasone therapy during both the treatment period and during a 5-week run-in period. Prior to randomization, patients were required to have evidence of bilateral polyps as determined by a nasal polyp score (NPS) ≥ 5 with NPS ≥ 2 in each nostril, despite use of nasal mometasone during the run-in period. NPS was measured via endoscopy and scored (range 0-4 per nostril: 0= no polyps; 1=small polyps in the middle meatus not reaching below the inferior border of the middle turbinate; 2=polyps reaching below the lower border of the middle turbinate; 3=large polyps reaching the lower border of the inferior turbinate or polyps medial to the middle turbinate; 4=large polyps causing complete obstruction of the inferior nasal cavity) for a total NPS (range 0-8). Patients were furthermore required to have a weekly average of nasal congestion score (NCS) > 1 prior to randomization, despite use of nasal mometasone. Nasal congestion was measured by a daily assessment on a 0 to 3 point severity scale (0=none, 1=mild, 2=moderate, 3=severe). Prior sino-nasal surgery or prior systemic corticosteroid usage were not required for inclusion in the trials and sinus CT scans were not performed to evaluate for sinus opacification. Demographics and baseline characteristics, including allergic comorbidities, are described in Table 14.

Table 14. Demographics and Baseline Characteristics of CRSwNP Trials 1 and 2
Parameter | CRSwNP Trial 1 (n=138) | CRSwNP Trial 2 (n=127)
Mean age (years) (SD) | 51 (13) | 50 (12)
% Male | 64 | 65
Patients with systemic corticosteroid use in the previous year (%) | 19 | 26
Patients with prior surgery for nasal polyps (%) | 79 (57) | 79 (62)
Mean bilateral endoscopic NPS (SD), range 0-8 | 6.2 (1.0) | 6.3 (0.9)
Mean nasal congestion score (SD) range 0-3 | 2.4 (0.6) | 2.3 (0.7)
Mean sense of smell score (SD) range 0-3 | 2.7 (0.7) | 2.7 (0.7)
Mean post nasal drip score (SD) range 0-3 | 1.8 (0.9) | 1.7 (0.9)
Mean runny nose score (SD) range 0-3 | 2.0 (0.8) | 1.9 (0.9)
Mean blood eosinophils (cells/mcL) (SD) | 346 (284) | 335 (188)
Mean total IgE IU/mL (SD) | 161 (140) | 190 (201)
Asthma (%) | 54 | 61
Aspirin exacerbated respiratory disease (%) | 20 | 35
CRSwNP= chronic rhinosinusitis with nasal polyps; SD=standard deviation; NPS=nasal polyp score; IgE = Immunoglobulin E; IU=international units. For NPS, NCS, sense of smell, post nasal drip, and runny nose, higher scores indicate greater disease severity.

The co-primary endpoints in CRSwNP Trials 1 and 2 were NPS and average daily NCS at Week 24. In both trials, patients who received XOLAIR had a statistically significant greater improvement from baseline at Week 24 in NPS and weekly average NCS, than patients who received placebo. Results from CRSwNP Trials 1 and 2 are shown in Table 15.

The greater improvements in NPS and NCS in the XOLAIR group compared to the placebo group were observed as early as the first assessment at Week 4 in both studies, as seen in Figure 1.

Table 15. Change from Baseline at Week 24 in Nasal Polyp Score and 7-day Average of Daily Nasal Congestion Score in CRSwNP Trials 1 and 2
 | Trial 1 |  | Trial 2
 | Placebo | XOLAIR | Placebo | XOLAIR
Number of patients | 65 | 72 | 65 | 62
Nasal Polyp Score
Mean Baseline Score | 6.3 | 6.2 | 6.1 | 6.4
LS Mean Change From Baseline at Week 24 | 0.1 | -1.1 | -0.3 | -0.9
Difference in LS means vs. placebo | -1.1 |  | -0.6
95% CI for difference | -1.6, -0.7 |  | -1.1, -0.1
p-value | <0.0001 |  | 0.0140
7-day Average of Daily Nasal Congestion Score
Mean Baseline Score | 2.5 | 2.4 | 2.3 | 2.3
LS Mean Change From Baseline at Week 24 | -0.4 | -0.9 | -0.2 | -0.7
Difference in LS means vs. placebo | -0.6 |  | -0.5
95% CI for difference | -0.8, -0.3 |  | -0.8, -0.2
p-value | 0.0004 |  | 0.0017
CRSwNP= chronic rhinosinusitis with nasal polyps; LS=least-square. Change from baseline was analyzed using a mixed-effect model of repeated measures (MMRM) model with baseline score, baseline score/timepoint (week) interaction as covariates, and the following factors: geographic region, asthma/aspirin sensitivity comorbidity status, timepoint, treatment group, treatment/timepoint interaction.

The mean NPS and NCS at each study week by treatment group is shown in Figure 1.

Figure 1. Mean Change from Baseline in Nasal Congestion Score and Mean Change from Baseline in Nasal Polyp Score by Treatment Group in CRSwNP Trials 1 and 2

XOLAIR had statistically significant improvements on sense of smell score compared to placebo. Sense of smell was measured by a daily assessment on a 0 to 3 point severity scale (0=no symptoms, 1=mild symptoms, 2=moderate symptoms, 3=severe symptoms). The LS mean difference for change from baseline at Week 24 in sense of smell score in XOLAIR compared to placebo was -0.3 (95% CI: -0.6, -0.1) in CRSwNP Trial 1 and -0.5 (95% CI: -0.7, -0.2) in CRSwNP Trial 2.

XOLAIR had statistically significant improvements on post-nasal drip compared to placebo. The LS mean difference for change from baseline at Week 24 in post-nasal drip score in XOLAIR compared to placebo was -0.6 (95% CI: -0.8, -0.3) in CRSwNP Trial 1 and -0.5 (95% CI: -0.8, -0.3) in CRSwNP Trial 2.

XOLAIR had statistically significant improvements on runny nose compared to placebo. The LS mean difference for change from baseline at Week 24 in runny nose score in XOLAIR compared to placebo was -0.4 (95% CI: -0.7, -0.2) in CRSwNP Trial 1 and -0.6 (95% CI: -0.9, -0.4) in CRsWNP Trial 2.

In a pre-specified pooled analysis of systemic corticosteroid use during the 24-week treatment period, there was no significant reduction in systemic corticosteroid use between the treatment arms. The proportion of patients taking systemic corticosteroid in XOLAIR was 2.3% compared to 6.2% in placebo. The odds-ratio of systemic corticosteroid use with XOLAIR compared to placebo was 0.4 (95% CI: 0.1, 1.5).

There were no sino-nasal surgeries reported, in either placebo or XOLAIR arms, in either Trial.

14.3 IgE-Mediated Food Allergy

The safety and efficacy of XOLAIR was evaluated in a multi-center, randomized, double-blind, placebo-controlled Food Allergy (FA) trial [NCT03881696] in 168 adult patients and pediatric patients 1 year of age to less than 56 years who were allergic to peanut and at least two other foods, including milk, egg, wheat, cashew, hazelnut, or walnut (i.e., studied foods). The FA trial enrolled patients who experienced dose-limiting symptoms (e.g., moderate to severe skin, respiratory or gastrointestinal symptoms) to a single dose of ≤100 mg of peanut protein and ≤300 mg protein for each of the other two foods (milk, egg, wheat, cashew, hazelnut, or walnut) during the screening double-blind placebo-controlled food challenge (DBPCFC). Patients with a history of severe anaphylaxis (defined as neurological compromise or requiring intubation) were excluded from the study. Patients were randomized 2:1 to receive a subcutaneous dosage of XOLAIR or placebo based on serum total IgE level (IU/mL), measured before the start of treatment, and by body weight according to Table 4 [see Dosage and Administration (2.4)] for 16 to 20 weeks. After 16 to 20 weeks of treatment, each patient completed a DBPCFC consisting of placebo and each of their 3 studied foods. Following the DBPCFC, the first 60 patients that included 59 pediatric patients and one adult patient who completed the double-blind, placebo-controlled phase of the study could continue to receive XOLAIR in a 24 to 28 week open-label extension.

Efficacy of XOLAIR is based on 165 pediatric patients who were included in the efficacy analyses provided below. The mean age of the pediatric patients was 8 years (age range: 1 to 17 years); 37% were less than 6 years of age, 38% were 6 to less than 12 years of age, and 25% were 12 to less than 18 years of age. Patient population were 56% male, 63% White, 13% Asian, 7% Black, 16% Other, and 55% of patients had a history of asthma.

The primary efficacy endpoint was the percentage of patients who were able to consume a single dose of ≥600 mg of peanut protein without dose-limiting symptoms (e.g., moderate to severe skin, respiratory or gastrointestinal symptoms) during DBPCFC. Table 16 shows XOLAIR treatment led to a statistically higher response rate (68%) than placebo (5%).

The secondary efficacy endpoints were the percentage of patients who were able to consume a single dose of ≥1000 mg of cashew, milk, or egg protein without dose-limiting symptoms during DBPCFC. The study met the secondary endpoints and demonstrated that XOLAIR treatment led to statistically higher response rates than placebo for all three foods. See Table 16 for details.

Table 16. DBPCFC Response Rates in Pediatric Patients for Single Dose of Peanut, Cashew, Milk or Egg Protein in FA Trial
Food, Challenge Dose | Response Rate [Response defined as consumption of a single dose of the specified amount of food without dose-limiting symptoms.] (%) (n/N) |  | Treatment Difference (%) (XOLAIR-Placebo) (95% CI)
Food, Challenge Dose | XOLAIR | Placebo | Treatment Difference (%) (XOLAIR-Placebo) (95% CI)
Peanut, ≥600 mg | 68% (75/110) | 5% (3/55) | 63% (50%, 73%)
Peanut, ≥1000 mg [Consumption of a single dose of ≥1000 mg of peanut protein was an additional secondary endpoint. The key secondary efficacy endpoints were the percentage of patients who were able to consume a single dose of ≥1000 mg of cashew, milk, or egg protein.] | 65% (72/110) | 0% (0/55) | 65% (56%, 74%)
Cashew, ≥1000 mg | 42% (27/64) | 3% (1/30) | 39% (20%, 53%)
Milk, ≥1000 mg | 66% (25/38) | 11% (2/19) | 55% (29%, 73%)
Egg, ≥1000 mg | 67% (31/46) | 0% (0/19) | 67% (49%, 80%)
CI = Confidence interval; DBPCFC = Double-blind placebo-controlled food challenge; n = Number of responders; N = Total number of patients receiving food, challenge dose.
Notes: Subjects without an exit DBPCFC or evaluable exit DBPCFC were counted as non-responders; P-values from two-sided Fisher's exact tests were <0.0001 for all the food challenge doses.

Seventeen percent of XOLAIR treated patients were not able to consume >100 mg of peanut protein without moderate to severe dose-limiting symptoms. Eighteen, 22, and 41 percent of XOLAIR-treated patients were not able to consume >300 mg of milk, egg, or cashew protein, respectively, without moderate to severe dose-limiting symptoms.

Additional secondary analyses included the percentage of patients who were able to consume at least two or all three foods during DBPCFC. For two foods, 71% of XOLAIR treated patients were able to consume a single dose of ≥600 mg versus 5% in the placebo group and 67% were able to consume a single dose of ≥1000 mg versus 4% in the placebo group. For a single dose of ≥600 mg of three foods, the response rates were 48% in the XOLAIR group versus 4% in the placebo group and for a single dose of ≥1000 mg of three foods, the response rate in the XOLAIR group was 39% while none of the placebo patients were able to consume the challenge dose without symptoms.

The effectiveness of XOLAIR in adults is supported by the adequate and well-controlled trial of XOLAIR in pediatric patients, disease similarity in pediatric and adult patients, and pharmacokinetic (PK) similarity [see Clinical Pharmacology (12.3)].

While efficacy cannot be established from uncontrolled, open-label studies, for 38 pediatric patients who continued XOLAIR for 24-28 weeks in an open-label extension, the percentage of patients who were able to consume ≥600 mg of peanut protein and ≥1000 mg of egg, milk, and/or cashew protein without moderate to severe dose-limiting symptoms was maintained.

14.4 Chronic Spontaneous Urticaria

Adult and Adolescent Patients 12 Years of Age and Older

The safety and efficacy of XOLAIR for the treatment of chronic spontaneous urticaria (CSU), previously referred to as chronic idiopathic urticaria (CIU) was assessed in two placebo-controlled, multiple-dose clinical trials of 24 weeks' duration (CSU Trial 1; n= 319, [NCT01287117]) and 12 weeks' duration (CSU Trial 2; n=322, [NCT01292473]). Patients received XOLAIR 75 mg, 150 mg, or 300 mg or placebo by SC injection every 4 weeks in addition to their baseline level of H1 antihistamine therapy for 24 or 12 weeks, followed by a 16-week washout observation period. A total of 640 patients (165 males, 475 females) were included for the efficacy analyses. Most patients were white (84%) and the median age was 42 years (range 12–72).

Disease severity was measured by a weekly urticaria activity score (UAS7, range 0–42), which is a composite of the weekly itch severity score (range 0–21) and the weekly hive count score (range 0–21). All patients were required to have a UAS7 of ≥16, and a weekly itch severity score of ≥8 for the 7 days prior to randomization, despite having used an H1 antihistamine for at least 2 weeks.

The mean weekly itch severity scores at baseline were fairly balanced across treatment groups and ranged between 13.7 and 14.5 despite use of an H1 antihistamine at an approved dose. The reported median durations of CSU at enrollment across treatment groups were between 2.5 and 3.9 years (with an overall subject-level range of 0.5 to 66.4 years).

In both CSU Trials 1 and 2, patients who received XOLAIR 150 mg or 300 mg had greater decreases from baseline in weekly itch severity scores and weekly hive count scores than placebo at Week 12. Representative results from CSU Trial 1 are shown (Table 17); similar results were observed in CSU Trial 2. The 75-mg dose did not demonstrate consistent evidence of efficacy and is not approved for use.

Table 17. Change from Baseline to Week 12 in Weekly Itch Severity Score and Weekly Hive Count Score in CSU Trial 1 [Modified intent-to-treat (mITT) population: all patients who were randomized and received at least one dose of study medication.]
 | XOLAIR 75mg | XOLAIR 150mg | XOLAIR 300mg | Placebo
N | 77 | 80 | 81 | 80
Weekly Itch Severity Score
Mean Baseline Score (SD) | 14.5 (3.6) | 14.1 (3.8) | 14.2 (3.3) | 14.4 (3.5)
Mean Change Week 12 (SD) | −6.46 (6.14) | −6.66 (6.28) | −9.40 (5.73) | −3.63 (5.22)
Difference in LS means vs. placebo | −2.96 | −2.95 | −5.80
95% CI for difference | −4.71, −1.21 | −4.72, −1.18 | −7.49, −4.10 | -
Weekly Hive Count Score [Score measured on a range of 0–21]
Mean Baseline Score (SD) | 17.2 (4.2) | 16.2 (4.6) | 17.1 (3.8) | 16.7 (4.4)
Mean Change Week 12 (SD) | −7.36 (7.52) | −7.78 (7.08) | −11.35 (7.25) | −4.37 (6.60)
Difference in LS means vs. placebo | −2.75 | −3.44 | −6.93
95% CI for difference | −4.95, −0.54 | −5.57, −1.32 | −9.10, −4.76 | -

The mean weekly itch severity score at each study week by treatment groups is shown in Figure 2. Representative results from CSU Trial 1 are shown; similar results were observed in CSU Trial 2. The appropriate duration of therapy for CSU with XOLAIR has not been determined.

Figure 2. Mean Weekly Itch Severity Score by Treatment Group Modified Intent to Treat Patients in CSU Trial 1

In CSU Trial 1, a larger proportion of patients treated with XOLAIR 300 mg (36%) reported no itch and no hives (UAS7=0) at Week 12 compared to patients treated with XOLAIR 150 mg (15%), XOLAIR 75 mg (12%), and placebo group (9%). Similar results were observed in CSU Trial 2.

16 HOW SUPPLIED/STORAGE AND HANDLING

Injection (Prefilled Syringe or Autoinjector)

XOLAIR (omalizumab) injection is a clear to slightly opalescent and colorless to pale brownish-yellow solution for subcutaneous use.

XOLAIR injection is provided as either a single-dose prefilled syringe with staked needle, rigid needle cap, and needle shield or a single-dose prefilled autoinjector with staked needle, needle cap and needle guard.

XOLAIR is available as prefilled syringe and autoinjector as described in Tables 18 and 19.

Table 18. XOLAIR Prefilled Syringe Strengths and Package Configurations
Package Configuration | Strength | NDC
1 prefilled syringe with a 26-gauge staked needle [The needle cap of the XOLAIR prefilled syringe contains a derivative of natural rubber latex which may cause allergic reactions in latex sensitive individuals.] | 75 mg/0.5 mL | NDC 50242-214-01
1 prefilled syringe with a 26-gauge staked needle | 150 mg/mL | NDC 50242-215-01
1 prefilled syringe with a 27-gauge staked needle | 75 mg/0.5 mL | NDC 50242-214-03
1 prefilled syringe with a 27-gauge staked needle | 150 mg/mL | NDC 50242-215-03
1 prefilled syringe with a 27-gauge staked needle | 300 mg/2 mL | NDC 50242-227-01

Table 19. XOLAIR Autoinjector Strengths and Package Configurations
Package Configuration | Strength | NDC
1 autoinjector with a 27-gauge staked needle | 75 mg/0.5 mL | NDC 50242-214-55
1 autoinjector with a 27-gauge staked needle | 150 mg/mL | NDC 50242-215-55
1 autoinjector with a 27-gauge staked needle | 300 mg/2 mL | NDC-50242-227-55

The XOLAIR autoinjector is not made with natural rubber latex.

Storage

XOLAIR prefilled syringe and autoinjector should be shipped and stored under refrigerated conditions 2°C to 8°C (36°F to 46°F) in the original carton. Protect from direct sunlight. XOLAIR prefilled syringe and autoinjector can be removed from and placed back in the refrigerator if needed. The total combined time out of the refrigerator may not be more than 2 days. Do not use if prefilled syringe or autoinjector is left at temperatures above 25°C (77°F).

Do not freeze. Do not use if the prefilled syringe or autoinjector has been frozen.

For Injection (Vial)

XOLAIR is supplied as a lyophilized, white, sterile powder in a single-dose vial without preservatives. Each carton contains:

- one single-dose vial of XOLAIR® (omalizumab) 150 mg for injection NDC 50242-040-62.

Storage

XOLAIR should be shipped at controlled ambient temperature (≤30°C [≤86°F]). Store XOLAIR under refrigerated conditions 2°C to 8°C (36°F to 46°F) in the original carton. Do not use beyond the expiration date stamped on carton.

17 PATIENT COUNSELING INFORMATION

Advise the patient to read the FDA-approved patient labeling (Medication Guide and Instructions for Use).

Anaphylaxis

Inform patients of the risk of life-threatening anaphylaxis with XOLAIR including the following points [see Boxed Warning and Warnings and Precautions (5.1)]:

- There have been reports of anaphylaxis occurring up to 4 days after administration of XOLAIR
- Initiate XOLAIR only in a healthcare setting by healthcare providers
- Observe patients closely following administration
- Inform patients of the signs and symptoms of anaphylaxis
- Instruct patients to seek immediate medical care should such signs or symptoms occur

Potential Medication Error Related to Emergency Treatment of Anaphylaxis

Advise patients, parents, or caregivers that XOLAIR should not be used for the emergency treatment of allergic reactions, including anaphylaxis [see Warnings and Precautions (5.9)].

Continuation of Other Medications

Instruct patients receiving XOLAIR not to decrease the dose of, or stop taking any other asthma, CRSwNP, CSU or IgE-mediated food allergy medications or allergen immunotherapy unless otherwise instructed by their physician. Inform patients that they may not see immediate improvement in their asthma, CRSwNP, CSU or IgE-mediated food allergy symptoms after beginning XOLAIR therapy.

Prefilled Syringe Needle Cover Contains Latex

Inform patients the needle cover on the prefilled syringe contains dry natural rubber (a derivative of latex), which may cause allergic reactions in individuals sensitive to latex [see How Supplied/Storage and Handling (16)].

Instruction on Injection Technique

If a patient or caregiver is to administer subcutaneous XOLAIR prefilled syringe or autoinjector, instruct on injection technique and assess ability to inject subcutaneously to ensure proper administration of XOLAIR. For patients who require more than 1 injection to complete their prescribed dose, instruct patients to administer all injections consecutively and in one sitting [see Dosage and Administration (2.7), Warnings and Precautions (5.1), and Instructions for Use].

Manufactured by:
Genentech, Inc.
A Member of the Roche Group
1 DNA Way
South San Francisco, CA 94080-4990
U.S. License No.:1048

MEDICATION GUIDE

XOLAIR® (ZOHL-air)
(omalizumab)
injection, for subcutaneous use

XOLAIR® (ZOHL-air)
(omalizumab)
for injection, for subcutaneous use

What is the most important information I should know about XOLAIR?
XOLAIR may cause serious side effects, including:
Severe allergic reaction. A severe allergic reaction called anaphylaxis can happen when you receive XOLAIR. The reaction can occur after the first dose, or after many doses. It may also occur right after a XOLAIR injection or days later. Anaphylaxis is a life-threatening condition and can lead to death. Go to the nearest emergency room right away if you have any of these symptoms of an allergic reaction:

- wheezing, shortness of breath, cough, chest tightness, or trouble breathing
- low blood pressure, dizziness, fainting, rapid or weak heartbeat, anxiety, or feeling of "impending doom"
- flushing, itching, hives, or feeling warm
- swelling of the throat or tongue, throat tightness, hoarse voice, or trouble swallowing

Your healthcare provider will monitor you closely for symptoms of an allergic reaction while you are receiving XOLAIR and for a period of time after treatment is initiated. Your healthcare provider should talk to you about getting medical treatment if you have symptoms of an allergic reaction.

What is XOLAIR?
XOLAIR is an injectable prescription medicine used to treat:

- moderate to severe persistent asthma in people 6 years of age and older whose asthma symptoms are not well controlled with asthma medicines called inhaled corticosteroids. A skin or blood test is performed to see if you have allergies to year-round allergens. It is not known if XOLAIR is safe and effective in people with asthma under 6 years of age.
- chronic rhinosinusitis with nasal polyps (CRSwNP) in people 18 years of age and older when medicines to treat CRSwNP called nasal corticosteroids have not worked well enough. It is not known if XOLAIR is safe and effective in people with CRSwNP under 18 years of age.
- food allergy in people 1 year of age and older to reduce allergic reactions that may occur after accidentally eating one or more foods to which you are allergic. While taking XOLAIR you should continue to avoid all foods to which you are allergic. It is not known if XOLAIR is safe and effective in people with food allergy under 1 year of age.
- chronic spontaneous urticaria (CSU, previously referred to as chronic idiopathic urticaria (CIU), chronic hives without a known cause) in people 12 years of age and older who continue to have hives that are not controlled with H1 antihistamine treatment. It is not known if XOLAIR is safe and effective in people with CSU under 12 years of age.

XOLAIR should not be used for the emergency treatment of any allergic reactions, including anaphylaxis. XOLAIR should also not be used to treat other forms of hives, or sudden breathing problems.

Who should not receive and use XOLAIR?
Do not receive and use XOLAIR if you:

- are allergic to omalizumab or any of the ingredients in XOLAIR. See the end of this Medication Guide for a complete list of ingredients in XOLAIR.

What should I tell my healthcare provider before receiving XOLAIR?
Before receiving XOLAIR, tell your healthcare provider about all of your medical conditions, including if you:

- have a latex allergy or any other allergies (such as seasonal allergies). The needle cap on the XOLAIR prefilled syringe contains a type of natural rubber latex.
- have sudden breathing problems (bronchospasm).
- have ever had a severe allergic reaction called anaphylaxis.
- have or have had a parasitic infection.
- have or have had cancer.
- are pregnant or plan to become pregnant. It is not known if XOLAIR may harm your unborn baby.
- are breastfeeding or plan to breastfeed. It is not known if XOLAIR passes into your breast milk. Talk with your healthcare provider about the best way to feed your baby while you receive and use XOLAIR.

Tell your healthcare provider about all the medicines you take, including prescription and over-the-counter medicines, vitamins, and herbal supplements.

How should I receive and use XOLAIR?

- When starting treatment XOLAIR should be given by your healthcare provider in a healthcare setting.
- If your healthcare provider decides that you or a caregiver may be able to give your own XOLAIR prefilled syringe or autoinjector injections, you should receive training on the right way to prepare and inject XOLAIR.
- Do not try to inject XOLAIR until you have been shown the right way to give XOLAIR prefilled syringe or autoinjector injections by a healthcare provider. Use XOLAIR exactly as prescribed by your healthcare provider.
- The XOLAIR autoinjector (all doses) is intended for use only in adults and adolescents aged 12 years and older. For children 12 years of age and older, XOLAIR prefilled syringe or autoinjector may be self-injected under adult supervision. For children 1 to 11 years of age, XOLAIR prefilled syringe should be injected by a caregiver.
- See the detailed Instructions for Use that comes with XOLAIR for information on the right way to prepare and inject XOLAIR.
- XOLAIR is given in 1 or more injections under the skin (subcutaneous), 1 time every 2 or 4 weeks.
- In people with asthma,CRSwNP and food allergy, a blood test for a substance called IgE must be performed before starting XOLAIR to determine the appropriate dose and dosing frequency.
- In people with chronic hives, a blood test is not necessary to determine the dose or dosing frequency.
- Do not decrease or stop taking any of your other asthma, CRSwNP, hive medicine, food allergy medicine or allergen immunotherapy unless your healthcare providers tell you to.
- You may not see improvement in your symptoms right away after XOLAIR treatment. If your symptoms do not improve or get worse, call your healthcare provider.
- If you inject more XOLAIR than prescribed, call your healthcare provider right away.

What are the possible side effects of XOLAIR?
XOLAIR may cause serious side effects, including:

- See "What is the most important information I should know about XOLAIR?"
- Cancer. Cases of cancer were observed in some people who received XOLAIR.
- Inflammation of your blood vessels. Rarely, this can happen in people with asthma who receive XOLAIR. This usually, but not always, happens in people who also take a steroid medicine by mouth that is being stopped or the dose is being lowered. It is not known whether this is caused by XOLAIR. Tell your healthcare provider right away if you have:

- rash
- shortness of breath

- chest pain
- a feeling of pins and needles or numbness of your arms or legs

- Fever, muscle aches, and rash. Some people get these symptoms 1 to 5 days after receiving a XOLAIR injection. If you have any of these symptoms, tell your healthcare provider.
- Parasitic infection. Some people who are at a high risk for parasite (worm) infections, get a parasite infection after receiving XOLAIR. Your healthcare provider can test your stool to check if you have a parasite infection.
- Heart and circulation problems. Some people who receive XOLAIR have had chest pain, heart attack, blood clots in the lungs or legs, or temporary symptoms of weakness on one side of the body, slurred speech, or altered vision. It is not known whether these are caused by XOLAIR.

The most common side effects of XOLAIR:

- In adults and children 12 years of age and older with asthma: joint pain especially in your arms and legs, dizziness, feeling tired, itching, skin rash, bone fractures, and pain or discomfort of your ears.
- In children 6 to less than 12 years of age with asthma: swelling of the inside of your nose, throat, or sinuses, headache, fever, throat infection, ear infection, abdominal pain, stomach infection, and nose bleeds.
- In adults with chronic rhinosinusitis with nasal polyps: headache, injection site reactions, joint pain, upper abdominal pain, and dizziness.
- In people with chronic spontaneous urticaria: nausea, headaches, swelling of the inside of your nose, throat or sinuses, cough, joint pain, and upper respiratory tract infection.
- In people with food allergy: injection site reactions and fever.

These are not all the possible side effects of XOLAIR. Call your doctor for medical advice about side effects. You may report side effects to FDA at 1-800-FDA-1088.

How should I store XOLAIR?

- Store XOLAIR in the refrigerator between 36°F to 46°F (2°C to 8°C).
- Keep your unused XOLAIR prefilled syringes or autoinjectors in the original carton until use to protect them from light.
- XOLAIR prefilled syringe or autoinjector can be removed from and placed back in the refrigerator if needed. The total combined time out of refrigerator may not be more than 2 days. Do not use if XOLAIR prefilled syringe or autoinjector is left at temperatures above 77°F (25°C) and discard in a sharps disposal container.
- Do not freeze. Do not use if XOLAIR prefilled syringes or autoinjectors have been frozen.
- Keep XOLAIR out of direct sunlight.
- Do not use XOLAIR past the expiration date.

Keep the XOLAIR prefilled syringe or autoinjector, sharps disposal container and all medicines out of the reach of children.

General information about the safe and effective use of XOLAIR.
Medicines are sometimes prescribed for purposes other than those listed in a Medication Guide. Do not use XOLAIR for a condition for which it was not prescribed. Do not give XOLAIR to other people, even if they have the same symptoms that you have. It may harm them. You can ask your pharmacist or healthcare provider for information about XOLAIR that is written for health professionals.
For more information, go to www.xolair.com or call 1-866-4XOLAIR (1-866-496-5247).

What are the ingredients in XOLAIR?
Active ingredient: omalizumab
Inactive ingredients:
Prefilled syringe or Autoinjector: arginine hydrochloride, histidine, L-histidine hydrochloride monohydrate, and polysorbate 20
Vial: histidine, L-histidine hydrochloride monohydrate, polysorbate 20 and sucrose
Manufactured by: Genentech, Inc., A Member of the Roche Group, 1 DNA Way, South San Francisco, CA 94080-4990. U.S. License No.: 1048
Jointly marketed by:
Genentech USA, Inc., A Member of the Roche Group, 1 DNA Way, South San Francisco, CA 94080-4990
Novartis Pharmaceuticals Corporation, One Health Plaza, East Hanover, NJ 07936-1080
XOLAIR® is a registered trademark of Novartis AG. ©2024 Genentech USA, Inc.

This Medication Guide has been approved by the U.S. Food and Drug Administration

Revised:2/2024

Instructions for Use
Xolair® (ZOHL-air)
(omalizumab)
injection, for subcutaneous use
Prefilled Syringe

Read this Instructions for Use before you start using the XOLAIR prefilled syringe and each time you get a refill. Before you use the XOLAIR prefilled syringe for the first time, make sure your healthcare provider shows you the right way to use it. Contact your healthcare provider if you have any questions.

Do not use XOLAIR for the emergency treatment of any allergic reactions, including anaphylaxis, hives, or sudden breathing problems.

Supplies needed to give your injection

- XOLAIR prefilled syringes (You may need more than 1 prefilled syringe for your prescribed dose). See "Choose the correct prefilled syringe or combination of prefilled syringes" for more information. Each XOLAIR carton contains 1 prefilled syringe.

The following supplies are not included in the carton:

- Alcohol swab
- Sterile cotton ball or gauze
- Small bandage
- Sharps disposal container (see step 14 "After the Injection")

Choose the correct prefilled syringe or combination of prefilled syringes
XOLAIR prefilled syringes are available in 2 dose strengths. These instructions are to be used for both dose strengths.
Your prescribed dose may require more than 1 injection. The table below shows the combination of prefilled syringes needed to give your full dose. Check the label on the XOLAIR carton to make sure you have received the correct prefilled syringe or combination of prefilled syringes for your prescribed dose. If your dose requires more than 1 injection, inject the medicine from all of your prescribed prefilled syringes, immediately one after another. Contact your healthcare provider if you have any questions.

How should I store XOLAIR?

- Keep your unused prefilled syringes in the original carton and store the carton in a refrigerator between 36°F to 46°F (2°C to 8°C). Do not remove the prefilled syringe from its original carton during storage.
- Before giving an injection, the carton can be removed from and placed back in the refrigerator if needed. The total combined time out of the refrigerator may not exceed 2 days. If the prefilled syringe is exposed to temperatures above 77 °F (25 °C), do not use it and throw away in a sharps disposal container.
- Keep your XOLAIR prefilled syringes out of direct sunlight.
- Do not freeze. Do not use if the prefilled syringe has been frozen.

Keep the XOLAIR prefilled syringe, sharps disposal container and all medicines out of the reach of children.

Important Information

- The needle cap contains a type of natural rubber latex. Tell your healthcare provider if you have a latex allergy.
- Do not open the sealed carton until you are ready to inject XOLAIR.
- Do not take the needle cap off until you are ready to inject XOLAIR.
- Do not try to take the prefilled syringe apart at any time.
- Do not reuse the same prefilled syringe.
- Do not leave the prefilled syringe unattended.

Preparing for the Injection

1 Take the carton containing the prefilled syringe out of the refrigerator.

- If your dose requires you to give more than 1 injection, take all cartons out of the refrigerator at the same time. The following steps must be followed for each prefilled syringe.

2 Check the expiration date on the XOLAIR carton.

- Do not use if the expiration date has passed.
  If the expiration date has passed, safely throw away the prefilled syringe in a sharps disposal container (see step 14) and contact your healthcare provider.

3 Place the carton on a clean, flat surface.

- Set aside the carton for at least 15 to 30 minutes so the prefilled syringe can warm up on its own to room temperature. Leave the prefilled syringe in the carton to protect it from light.
- If the prefilled syringe does not reach room temperature, this could cause the injection to feel uncomfortable and make it hard to push the plunger.
- Do not speed up the warming process using any heat sources such as warm water or a microwave.

4 Open the carton.

- Wash your hands with soap and water.
- Take the blister pack out of the carton.

- Check the expiration date on the blister pack.
- Do not use it if the expiration date has passed.
  If the expiration date has passed, safely throw away the prefilled syringe in a sharps disposal container (see step 14) and contact your healthcare provider.

- Peel off the blister pack cover fully. Be careful when taking out the prefilled syringe.
- Do not flip the blister pack upside down to take out the prefilled syringe. This may damage the prefilled syringe.
- Take the prefilled syringe out of the blister pack by holding the middle part of the prefilled syringe. When holding the prefilled syringe, make sure you always hold the prefilled syringe as shown. Do not touch the needle-shield wings (see "Prefilled Syringe Parts").
- Do not handle the prefilled syringe by holding the plunger or needle cap.

5 Inspect the prefilled syringe closely.

- Check the prefilled syringe. The medicine in the prefilled syringe should be clear and colorless to pale brownish-yellow. Do not use the prefilled syringe if the medicine is cloudy, discolored, or contains particles.
- Check the expiration date on the prefilled syringe. Do not use the prefilled syringe if the expiration date has passed.
- If the medicine does not look as described or if the expiration date has passed, safely throw away the prefilled syringe in a sharps disposal container (see step 14) and contact your healthcare provider.
- Do not use if the packaging or prefilled syringe appears damaged, tampered with, or has been dropped.

6 Choose an injection site.

- If you are giving yourself the injection, you can inject into the front and middle of the thighs and the stomach area (abdomen). The outer area of the upper arms may also be used if the injection is being given by a caregiver. Do not try to inject into the upper arm area by yourself.
- Do not inject within the 2-inch area directly around your belly button (navel).
- Do not inject into moles, scars, bruises, or areas where the skin is tender, red, hard, or if there are breaks in the skin.
- Do not inject through clothing. The injection site should be exposed, clean skin.
- If your prescribed dose requires more than 1 injection, choose a different injection site for each new injection, at least 1 inch from other injection sites.

7 Wipe the injection site with an alcohol swab in a circular motion and let it air dry for 10 seconds.

- Do not touch the injection site again before giving the injection.
- Do not fan or blow on the cleaned skin.

Giving the Injection

8 Hold the prefilled syringe firmly by the center with 1 hand and pull the needle cap straight off with your other hand.

- Do not twist the needle cap.
- Do not hold, push or pull the plunger while you remove the needle cap.
- Do not touch the needle or let it touch any surfaces after removing the needle cap.
- Throw away the needle cap in regular household trash. Do not recap the needle.
- There may be 1 or more small air bubbles in the prefilled syringe. This is normal, and you should not try to remove the air bubbles.
- You may also see a drop of liquid at the end of the needle. This is also normal and will not affect the dose.

9 Use your other hand and gently pinch the area of skin that was cleaned. Hold the pinched skin tight.

- Pinching the skin is important to make sure that you inject under the skin (into the fatty area) but not any deeper (into muscle).

10 Continue holding the prefilled syringe by the center and use a quick, dart-like motion to insert the needle all the way into the pinched skin at an angle between 45 degrees to 90 degrees as shown.

- It is important to use the correct angle to make sure the medicine is delivered under the skin (into the fatty area), or the injection could be uncomfortable and the medicine may not work.
- Do not touch the plunger while inserting the needle into the skin.
- Do not insert the needle through clothing.
- Hold the prefilled syringe tightly in place and do not change the angle of injection or insert the needle again after the needle is inserted.
- You should not move and should avoid sudden movements when giving the injection.

11 Slowly inject all of the medicine by gently pushing the plunger all the way down until the needle-shield wings are pushed apart.

- You must press the plunger all the way down to make sure that the full dose of medicine gets injected. If the plunger is not fully pressed, the needle-shield will not extend to cover the needle when it is removed.

12 Release the plunger and allow the needle to be covered by the needle-shield.

- If the needle is not covered by the needle-shield, carefully remove the prefilled syringe from the skin and throw away the prefilled syringe in a sharps disposal container (see step 14).

13 There may be a little bleeding at the injection site. You can press a cotton ball or gauze over the injection site.

- Do not rub the injection site.
- If needed, cover the injection site with a small bandage.
- In case of skin contact with the medicine, wash the area that touched the medicine with water.

If your prescribed dose requires more than 1 injection:

- Throw away the used prefilled syringe as described in step 14.
- Repeat step 2 through step 13 for the next injection using a new prefilled syringe.
- Choose a different injection site for each new injection at least 1 inch from other injection sites.
- Complete all the required injections for your prescribed dose, immediately one after another. Contact your healthcare provider if you have any questions.

After the Injection

14 Throw away (dispose of) your used XOLAIR prefilled syringes in an FDA-cleared sharps disposal container right away after use.

- The XOLAIR prefilled syringe is a single-dose prefilled syringe and should not be used again.
- Do not throw away prefilled syringes in your household trash.
- Do not recap the needle.

If you do not have an FDA-cleared sharps disposal container, you may use a household container that is:

- made of a heavy-duty plastic,
- can be closed with a tight-fitting, puncture-resistant lid, without sharps being able to come out,
- upright and stable during use,
- leak-resistant, and
- properly labeled to warn of hazardous waste inside the container.
- When your sharps disposal container is almost full, you will need to follow your community guidelines for the right way to dispose of your sharps disposal container. There may be state or local laws about how you should throw away used prefilled syringes. For more information about safe sharps disposal, and for specific information about sharps disposal in the state that you live in, go to the FDA's website at: http://www.fda.gov/safesharpsdisposal
- Do not dispose of your used sharps disposal container in your household trash unless your community guidelines permit this.
- Do not recycle your used sharps disposal container.

Manufactured by:
Genentech, Inc., A Member of the Roche Group,
1 DNA Way, South San Francisco, CA 94080-4990
U.S. License No.: 1048

Jointly marketed by:
Genentech USA, Inc., A Member of the Roche Group,
1 DNA Way, South San Francisco, CA 94080-4990
Novartis Pharmaceuticals Corporation,
One Health Plaza, East Hanover, NJ 07936-1080

XOLAIR® is a registered trademark of Novartis AG.
©2024 Genentech USA, Inc.

This Instructions for Use has been approved by the U.S. Food and Drug Administration.

Revised: 2/2024

Instructions for Use
Xolair® (ZOHL-air)
(omalizumab)
injection, for subcutaneous use
Prefilled Syringe

Read this Instructions for Use before you start using Xolair prefilled syringe and each time you get a refill. Before you use Xolair prefilled syringe for the first time, make sure your healthcare provider shows you the right way to use it. Contact your healthcare provider if you have any questions.

Do not use Xolair for the emergency treatment of any allergic reactions, including anaphylaxis, hives, or sudden breathing problems.

Prefilled Syringe Parts

Supplies needed to give your injection

- Xolair prefilled syringe .

The following supplies are not included in the carton:

- Alcohol swab
- Sterile cotton ball or gauze
- Small bandage
- Sharps disposal container (see Step 14)

Note: You may need more than 1 Xolair prefilled syringe for your prescribed dose. See the Dosing Table for more information. Each Xolair carton contains 1 prefilled syringe.

Choose the correct prefilled syringe or combination of prefilled syringes
Xolair prefilled syringes are available in 3 dose strengths (1 prefilled syringe in each carton). These instructions are to be used for all 3 dose strengths.
Your prescribed dose may require more than 1 injection. The Dosing Table below shows the combination of prefilled syringes needed to give your full dose. Check the label on the Xolair carton to make sure you have received the correct prefilled syringe or combination of prefilled syringes for your prescribed dose. If your dose requires more than 1 injection, complete all injections for your prescribed dose, immediately one after another. Contact your healthcare provider if you have any questions.

Dosing Table

Note: Your healthcare provider may prescribe a different combination of syringes for your complete dose.

How should I store Xolair?

- Keep your unused prefilled syringes in the original carton and store the carton in a refrigerator between 36°F to 46°F (2°C to 8°C). Do not remove the prefilled syringe from its original carton during storage.
- Before giving an injection, the carton can be removed from and placed back in the refrigerator if needed. The total combined time out of the refrigerator may not be more than 2 days. If the prefilled syringe is left at temperatures above 77°F (25°C), do not use it and throw away in a sharps disposal container.
- Keep your prefilled syringes out of direct light.
- Do not freeze. Do not use if the prefilled syringe has been frozen.

Keep the Xolair prefilled syringe, sharps disposal container and all medicines out of the reach of children.
Important Information

- Do not use if the carton is damaged or appears to be tampered with.
- Do not open the carton until you are ready to inject.
- Do not use if the prefilled syringe is damaged or appears to be tampered with.
- Do not take the needle cap off until you are ready to inject.
- Do not use if the prefilled syringe has been dropped on a hard surface or dropped after removing the needle cap.
- Do not try to take apart the prefilled syringe at any time.

Preparing for the Injection

1 Take the carton containing the prefilled syringe out of the refrigerator.

- If you need more than 1 prefilled syringe to deliver your full dose (see Dosing Table), take all cartons out of the refrigerator at the same time (each carton contains 1 prefilled syringe). The following steps must be followed for each prefilled syringe.

2 Check the expiration date on the Xolair carton.

- Do not use if the expiration date has passed.
- If the expiration date has passed, safely throw away the prefilled syringe in a sharps disposal container (see Step 14) and contact your healthcare provider.

3 Allow the prefilled syringe to reach room temperature.

- Set aside the carton on a clean, flat surface for at least 30 to 45 minutes so the prefilled syringe can warm up on its own to room temperature. Leave the prefilled syringe in the carton to protect it from light.
- If the prefilled syringe does not reach room temperature, this could cause the injection to feel uncomfortable and make it hard to push the plunger.
- Do not speed up the warming process using any heat sources such as warm water or a microwave.

4 Open the carton.

- Wash your hands with soap and water.
- Take the blister pack out of the carton.

- Check the expiration date on the blister pack.
- Do not use it if the expiration date has passed.
  If the expiration date has passed, safely throw away the prefilled syringe in a sharps disposal container (see Step 14) and contact your healthcare provider.

- Peel off the blister pack cover fully. Be careful when taking out the prefilled syringe.
- Do not flip the blister pack upside down to take out the prefilled syringe.
- Take the prefilled syringe out of the blister pack by holding the middle part of the prefilled syringe, as shown.
- Do not handle the prefilled syringe by holding the plunger or needle cap.

5 Inspect the prefilled syringe closely.

- Check the prefilled syringe. The medicine inside should be clear and colorless to pale brownish-yellow. You may see air bubbles in the medicine, which is normal. Do not try to remove the air bubbles.
- Do not use the prefilled syringe if the medicine contains particles, or if the medicine looks cloudy or brown.
- Check the expiration date on the prefilled syringe. Do not use the prefilled syringe if the expiration date has passed.
- Do not use if the prefilled syringe appears to be damaged or tampered with.
- If the medicine does not look as described or if the expiration date has passed, safely throw away the prefilled syringe in a sharps disposal container (see Step 14) and contact your healthcare provider.

6 Choose where to inject.

- If giving yourself the injection, the injection sites are the front of your thigh or stomach area (abdomen). If a caregiver is giving the injection, the injection sites are the outer area of the upper arm, the front of the thigh, or the stomach area (abdomen). Do not try to inject yourself in the upper arm.
- Do not inject within the 2-inch area directly around your belly button (navel).
- Do not inject into moles, scars, bruises, or areas where the skin is tender, red, hard, or if there are breaks in the skin.
- Do not inject through clothing. The injection site should be uncovered, clean skin.
- If your prescribed dose requires more than 1 injection, make sure your injections are at least 1 inch apart from each other.

7 Clean the injection site.

- Wipe the injection site with an alcohol swab in a circular motion and let air dry for 10 seconds.
- Do not fan or blow on the cleaned skin.
- Do not touch the injection site again before giving the injection.

Giving the Injection

8 Remove the cap.

- Hold the prefilled syringe firmly with 1 hand and pull the needle cap straight off with your other hand as shown. Do not twist the cap.
- Do not hold, push or pull the plunger while you remove the needle cap.
- Do not touch the needle or let it touch any surfaces after removing the needle cap.
- Do not put the cap back on the prefilled syringe. Throw away the needle cap in regular household trash.
- You may see a drop of liquid at the end of the needle. This is normal.

9 Pinch cleaned skin.

- Use your other hand and gently pinch the area of skin that was cleaned. Hold the pinched skin tightly until the injection is complete.
- Pinching the skin is important to make sure that you inject under the skin (into the fatty area) but not any deeper (into muscle).

10 Insert the needle using a quick, dart-like motion.

- While holding the prefilled syringe by the center, insert the needle all the way into the pinched skin at an angle of about 45 degrees as shown.
- It is important to use the correct angle to make sure the medicine is delivered under the skin (into the fatty area), or the injection could be uncomfortable and the medicine may not work.
- Do not touch the plunger while inserting the needle into the skin.
- Hold the prefilled syringe tightly in place and do not change the angle of injection or insert the needle again after the needle is inserted.
- You should not move and should avoid sudden movements when giving the injection.

11 Slowly inject all of the medicine.

- Gently push the plunger all the way down until the plunger head is between the safety guard wings as shown.
- You must press the plunger all the way down to make sure that the full dose of medicine is injected. If the plunger is not fully pressed, the needle-shield will not extend to cover the needle when it is removed.

12 Release the plunger.

- Release the plunger and allow the needle to be covered by the needle-shield.
- If the needle is not covered by the needle-shield, carefully remove the prefilled syringe from the skin and throw away the prefilled syringe in a sharps disposal container (see Step 14).

13 Care for the injection site.

- Do not rub the injection site.
- There may be a little bleeding or drop of liquid at the injection site. You can press a cotton ball or gauze over the injection site until the bleeding stops.
- In case of skin contact with the medicine, wash the area that touched the medicine with water.
- If needed, cover the injection site with a small bandage.

If your prescribed dose requires more than 1 injection:

- Throw away the used prefilled syringe as described in Step 14.
- Repeat Step 2 through Step 13 for the next injection using a new prefilled syringe.
- Make sure each injection is at least 1 inch apart from each other.
- Complete all the required injections for your prescribed dose, immediately one after another. Contact your healthcare provider if you have any questions.

After the Injection

14 Throw away (dispose of) the prefilled syringe.

- Put your used prefilled syringes in an FDA-cleared sharps disposal container right away after use.
- The Xolair prefilled syringe is a single-dose prefilled syringe and should not be used again.
- Do not throw away the prefilled syringes in your household trash.
- Do not recap the needle.

If you do not have an FDA-cleared sharps disposal container, you may use a household container that is:

- made of a heavy-duty plastic,
- can be closed with a tight-fitting, puncture-resistant lid, without sharps being able to come out,
- upright and stable during use,
- leak-resistant, and
- properly labeled to warn of hazardous waste inside the container.
- When your sharps disposal container is almost full, you will need to follow your community guidelines for the right way to dispose of your sharps disposal container. There may be state or local laws about how you should throw away used prefilled syringes. For more information about safe sharps disposal, and for specific information about sharps disposal in the state that you live in, go to the FDA's website at: http://www.fda.gov/safesharpsdisposal
- Do not dispose of your used sharps disposal container in your household trash unless your community guidelines permit this.
- Do not recycle your used sharps disposal container.

Manufactured by:
Genentech, Inc., A Member of the Roche Group,
1 DNA Way, South San Francisco, CA 94080-4990
U.S. License No.: 1048

Jointly marketed by:
Genentech USA, Inc., A Member of the Roche Group,
1 DNA Way, South San Francisco, CA 94080-4990
Novartis Pharmaceuticals Corporation,
One Health Plaza, East Hanover, NJ 07936-1080

Xolair® is a registered trademark of Novartis AG.
©2024 Genentech USA, Inc.

This Instructions for Use has been approved by the U.S. Food and Drug Administration.

Approved: 2/2024

Instructions for Use
Xolair® (ZOHL-air)
(omalizumab)
injection, for subcutaneous use
Autoinjector

Read this Instructions for Use before you start using Xolair autoinjector and each time you get a refill. Before you use Xolair autoinjector for the first time, make sure your healthcare provider shows you the right way to use it. Contact your healthcare provider if you have any questions.

The Xolair autoinjector is for use in people 12 years of age and older.

Do not use Xolair for the emergency treatment of any allergic reactions, including anaphylaxis, hives, or sudden breathing problems.

Xolair Autoinjector Parts

Supplies needed to give your injection

- Xolair autoinjector

The following supplies are not included in the carton:

- Alcohol swab
- Sterile cotton ball or gauze
- Small bandage
- Sharps disposal container (see Step 15)

Note: You may need more than 1 Xolair autoinjector to give your prescribed dose. See the Dosing Table for more information. Each Xolair carton contains 1 autoinjector.

Choose the correct autoinjector or combination of autoinjectors

Xolair autoinjectors are available in 3 dose strengths (1 autoinjector in each carton). These instructions are to be used for all 3 dose strengths.

Your prescribed dose may require more than 1 injection. The Dosing Table below shows the combination of autoinjectors needed to give your full dose. Check the label on the Xolair carton to make sure you have received the correct autoinjector or combination of autoinjectors for your prescribed dose. If your dose requires more than 1 injection, complete all injections for your prescribed dose, immediately one after another. Contact your healthcare provider if you have any questions.

Dosing Table

Note: Your healthcare provider may prescribe a different combination of autoinjectors for your complete dose.

How should I store Xolair?

- Keep your unused autoinjectors in the original carton and store the carton in a refrigerator between 36°F to 46°F (2°C to 8°C).
- Before giving an injection, the carton can be removed from and placed back in the refrigerator if needed. The total combined time out of the refrigerator may not be more than 2 days. If the autoinjector is left at temperatures above 77°F (25°C), do not use it and throw away in a sharps disposal container.
- Do not remove the autoinjector from its original carton during storage.
- Keep your autoinjectors out of direct light.
- Do not freeze. Do not use if the autoinjector has been frozen.

Keep the Xolair autoinjector, sharps disposal container and all medicines out of the reach of children.

Important Information

- Do not use if the carton is damaged or appears to be tampered with.
- Do not open the carton until you are ready to inject.
- Do not use if the autoinjector has been damaged or appears to be tampered with.
- Do not take the cap off the autoinjector until you are ready to inject.
- Do not use if the autoinjector has been dropped on a hard surface or dropped after removing the needle cap.
- Do not take apart the autoinjector at any time.
- Do not clean or touch the needle guard.

Preparing for the Injection

1 Take the carton containing the autoinjector out of the refrigerator.

- If you need more than 1 autoinjector to deliver your prescribed dose (see Dosing Table), take all cartons out of the refrigerator at the same time (each carton contains 1 autoinjector). The following steps must be followed for each autoinjector.

2 Check the expiration date on the back of the Xolair carton.

- Do not use if the expiration date has passed.
- If the expiration date has passed, safely throw away the autoinjector in a sharps disposal container (see Step 15) and contact your healthcare provider.

3 Allow the autoinjector to reach room temperature.

- Set aside the carton on a clean, flat surface for at least 30 to 45 minutes so the autoinjector can warm up on its own to room temperature. Leave the autoinjector in the carton to protect it from light.
- If the autoinjector does not reach room temperature, this could cause the injection to feel uncomfortable.
- Do not speed up the warming process using any heat sources such as warm water or a microwave.

4 Open the carton.

- Wash your hands with soap and water.
- Take the autoinjector out of the carton as shown.
- Do not turn the carton upside down to take out the autoinjector, as this may damage the autoinjector.
- Do not hold the autoinjector by the cap. Make sure you hold the autoinjector by the middle as shown.
- Do not remove the cap until you are ready to inject.

5 Check the autoinjector before use.

- Look through the viewing window of the autoinjector. The medicine in the autoinjector viewing window should be clear and colorless to pale brownish-yellow. You may see air bubbles in the medicine, which is normal.
- Do not use the autoinjector if the medicine contains particles, or if the medicine looks cloudy or brown.
- Check the expiration date on the autoinjector. Do not use the autoinjector if the expiration date has passed.
- Do not use the autoinjector if it appears to be damaged or tampered with.
- If the medicine does not look as described or if the expiration date has passed, safely throw away the autoinjector in a sharps disposal container (see Step 15) and contact your healthcare provider.

6 Choose where to inject.

- If giving yourself the injection, the injection sites are the front of your thigh or stomach area (abdomen). If a caregiver is giving the injection, the injection sites are the outer area of the upper arm, the front of the thigh or stomach area (abdomen). Do not try to inject yourself in the upper arm.
- Do not inject within the 2-inch area directly around your belly button (navel).
- Do not inject into moles, scars, bruises, or areas where the skin is tender, red, hard, or if there are breaks in the skin.
- Do not inject through clothing. The injection site should be uncovered, clean skin.
- If your prescribed dose requires more than 1 injection, make sure your injections are at least 1 inch apart from each other.

7 Clean the injection site.

- Wipe the injection site with an alcohol swab in a circular motion and let it air dry for 10 seconds.
- Do not fan or blow on the cleaned skin.
- Do not touch the injection site again before giving the injection.

Giving the Injection

8 Remove the cap.

- Hold the autoinjector firmly with 1 hand and pull the cap straight off with your other hand as shown. Do not twist the cap.
- Do not put the cap back on the autoinjector. Throw away the cap in regular household trash.
- Do not clean or touch the needle guard of the device.

9 Position the autoinjector.

- Hold the autoinjector comfortably with the needle guard directly against the skin.
- The autoinjector should be at a 90-degree angle against the skin, as shown.

10 Start the injection.

- Press straight down and hold the autoinjector firmly against the skin. The 1st click indicates that the injection has started.
- Hold the autoinjector tightly in place. Do not change the angle of injection or remove the autoinjector until the injection is completed.

11 Monitor injection using green indicator.

- Keep holding the autoinjector against the skin. The green indicator will move within the viewing window.

12 Complete injection.

- Listen for the 2nd click. This indicates that the injection is almost complete.
- Hold the autoinjector in position until the green indicator has stopped moving and completely fills the viewing window to make sure the injection is complete.

13 Remove from skin and check the green indicator.

- After the green indicator has stopped moving and has completely filled the viewing window, lift the autoinjector straight up from the skin. The needle guard will automatically extend and lock over the needle.
- If the green indicator has not completely filled the viewing window, contact your healthcare provider or pharmacist.

14 Care for the injection site.

- Do not rub the injection site.
- There may be a little bleeding or a drop of liquid at the injection site. You can press a cotton ball or gauze pad over the injection site until any bleeding stops.
- In case of skin contact with the medicine, wash the area that touched the medicine with water.
- If needed, cover the injection site with a small bandage.

If your prescribed dose requires more than 1 injection:

- Throw away the used autoinjector as described in Step 15.
- Repeat Step 2 through Step 14 for the next injection using a new autoinjector.
- Make sure each injection is at least 1 inch apart from each other.
- Complete all the required injections for your prescribed dose, immediately one after another. Contact your healthcare provider if you have any questions.

After the Injection

15 Throw away (dispose of) autoinjector.

- Put your used autoinjectors in an FDA-cleared sharps disposal container right away after use.
- The Xolair autoinjector is a single-dose autoinjector and should not be used again.
- Do not throw away (dispose of) the autoinjectors in your household trash.
- Do not recap the autoinjector.

If you do not have an FDA-cleared sharps disposal container, you may use a household container that is:

- made of a heavy-duty plastic,
- can be closed with a tight-fitting, puncture-resistant lid, without sharps being able to come out,
- upright and stable during use,
- leak-resistant, and
- properly labeled to warn of hazardous waste inside the container.
- When your sharps disposal container is almost full, you will need to follow your community guidelines for the right way to dispose of your sharps disposal container. There may be state or local laws about how you should throw away used autoinjectors. For more information about safe sharps disposal, and for specific information about sharps disposal in the state that you live in, go to the FDA's website at: http://www.fda.gov/safesharpsdisposal
- Do not dispose of your used sharps disposal container in your household trash unless your community guidelines permit this.
- Do not recycle your used sharps disposal container.

Manufactured by:
Genentech, Inc., A Member of the Roche Group,
1 DNA Way, South San Francisco, CA 94080-4990
U.S. License No.: 1048

Jointly marketed by:
Genentech USA, Inc., A Member of the Roche Group,
1 DNA Way, South San Francisco, CA 94080-4990
Novartis Pharmaceuticals Corporation,
One Health Plaza, East Hanover, NJ 07936-1080

Xolair® is a registered trademark of Novartis AG.
©2024 Genentech USA, Inc.

This Instructions for Use has been approved by the U.S. Food and Drug Administration.

Approved: 2/2024

Representative sample of labeling (see the HOW SUPPLIED section for complete listing):

PRINCIPAL DISPLAY PANEL - 150 mg Vial Carton

NDC 50242-040-62
SINGLE-DOSE VIAL

150 mg

Xolair®
Omalizumab
FOR SUBCUTANEOUS USE

KEEP REFRIGERATED. DO NOT FREEZE.

Genentech

NOVARTIS

10198215

PRINCIPAL DISPLAY PANEL - 75 mg/0.5 mL Syringe Carton - 214-01

Xolair®
(omalizumab) Injection

75 mg/0.5 mL

For Subcutaneous Use. Single-Dose Prefilled Syringe.

Dispense the accompanying
Medication Guide to each patient.

1 prefilled syringe

Do not use for emergency treatment.
Your dose may require more than 1 injection.
For questions, contact your healthcare provider.

NDC 50242-214-01

Caution: The needle cap may contain natural rubber latex
which may cause allergic reactions in latex sensitive individuals.

Rx only

Genentech

NOVARTIS

11011555

PRINCIPAL DISPLAY PANEL - 75 mg/0.5 mL Syringe Carton - 214-03

Xolair®
(omalizumab) Injection

75 mg/0.5 mL

For Subcutaneous Use.

1 Single-Dose Prefilled Syringe

Do not use for emergency treatment.
Your dose may require more than 1 injection.
For questions, contact your healthcare provider.

NDC 50242-214-03

Dispense the accompanying Medication Guide to each patient.

Rx only

Must be refrigerated

Genentech

NOVARTIS

11011485

PRINCIPAL DISPLAY PANEL - 75 mg/0.5 mL Autoinjector Carton

Xolair®
(omalizumab) Injection

75 mg/0.5 mL

For Subcutaneous Use.

1 Single-Dose Autoinjector

Do not use for emergency treatment.
Your dose may require more than 1 injection.
For questions, contact your healthcare provider.

NDC 50242-214-55

Dispense the accompanying Medication Guide to each patient.

Genentech

NOVARTIS

11011505

PRINCIPAL DISPLAY PANEL - 150 mg/mL Syringe Carton - 215-01

Xolair®
(omalizumab) Injection

150 mg/mL

For Subcutaneous Use. Single-Dose Prefilled Syringe.

Dispense the accompanying
Medication Guide to each patient.

1 prefilled syringe

Do not use for emergency treatment.
Your dose may require more than 1 injection.
For questions, contact your healthcare provider.

NDC 50242-215-01

Caution: The needle cap may contain natural rubber latex
which may cause allergic reactions in latex sensitive individuals.

Rx only

Genentech

NOVARTIS

11011498

PRINCIPAL DISPLAY PANEL - 150 mg/mL Syringe Carton - 215-03

Xolair®
(omalizumab) Injection

150 mg/mL

For Subcutaneous Use.

1 Single-Dose Prefilled Syringe

Do not use for emergency treatment.
Your dose may require more than 1 injection.
For questions, contact your healthcare provider.

NDC 50242-215-03

Dispense the accompanying Medication Guide to each patient.

Rx only

Must be refrigerated

Genentech

NOVARTIS

11011522

PRINCIPAL DISPLAY PANEL - 150 mg/mL Autoinjector Carton

Xolair®
(omalizumab) Injection

150 mg/mL

For Subcutaneous Use.

1 Single-Dose Autoinjector

Do not use for emergency treatment.
Your dose may require more than 1 injection.
For questions, contact your healthcare provider.

NDC 50242-215-55

Dispense the accompanying Medication Guide to each patient.

Genentech

NOVARTIS

11011532

PRINCIPAL DISPLAY PANEL - 300 mg/2 mL Syringe Carton

Xolair®
(omalizumab) Injection

300 mg/2 mL

For Subcutaneous Use.

1 Single-Dose Prefilled Syringe

Do not use for emergency treatment.
Your dose may require more than 1 injection.
For questions, contact your healthcare provider.

NDC 50242-227-01

Dispense the accompanying Medication Guide to each patient.

Rx only

Must be refrigerated

Genentech

NOVARTIS

11011496

PRINCIPAL DISPLAY PANEL - 300 mg/2 mL Autoinjector Carton

Xolair®
(omalizumab) Injection

300 mg/2 mL

For Subcutaneous Use.

1 Single-Dose Autoinjector

Do not use for emergency treatment.
Your dose may require more than 1 injection.
For questions, contact your healthcare provider.

NDC 50242-227-55

Dispense the accompanying Medication Guide to each patient.

Genentech

NOVARTIS

11011548